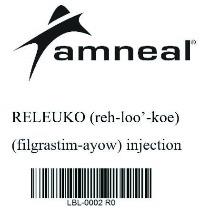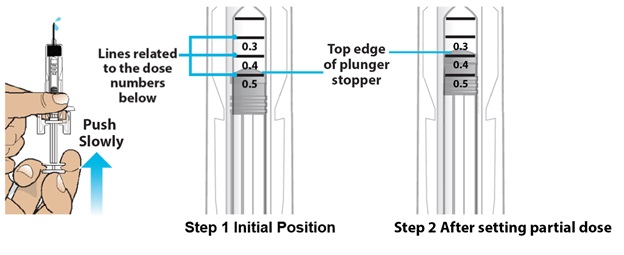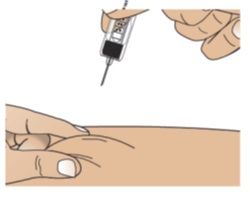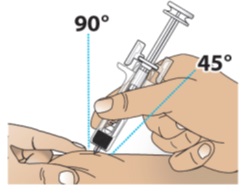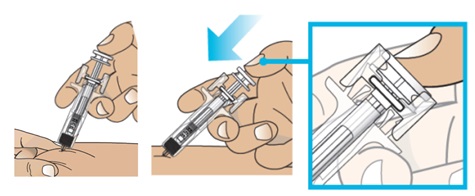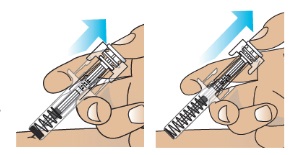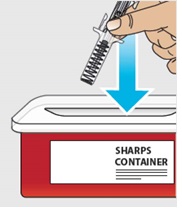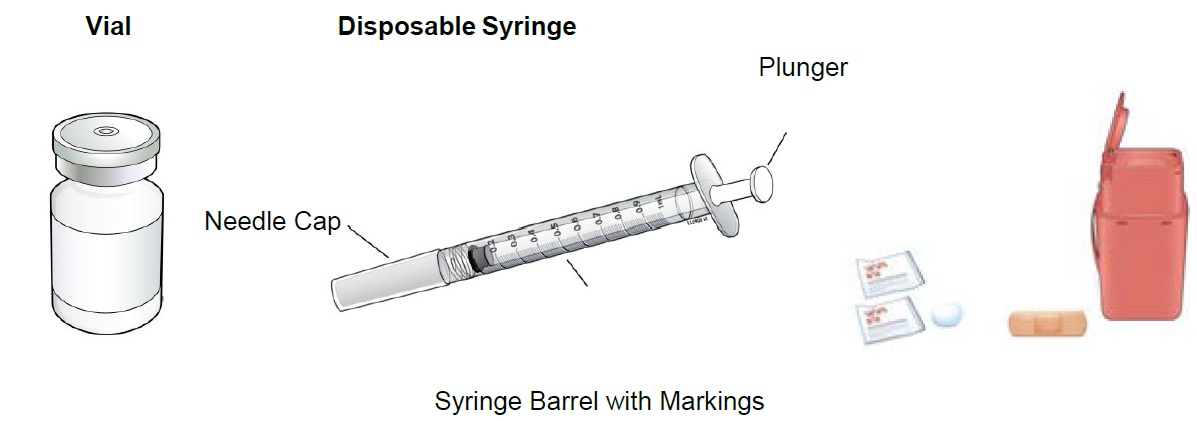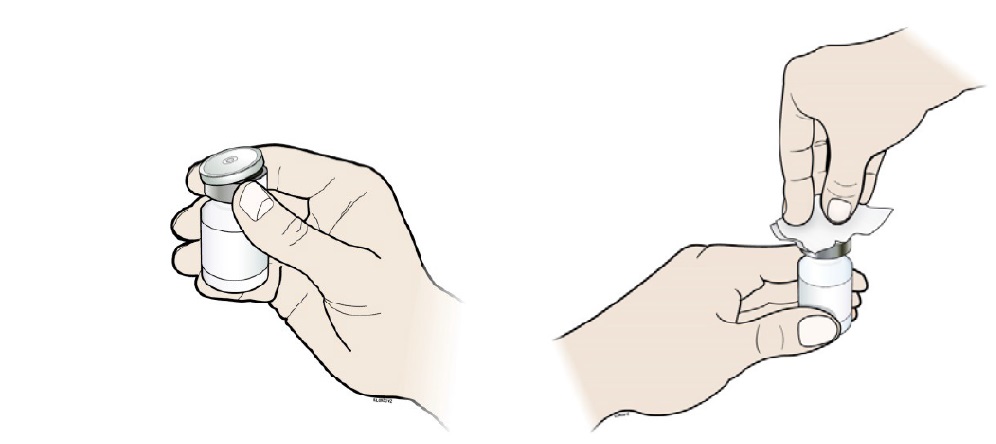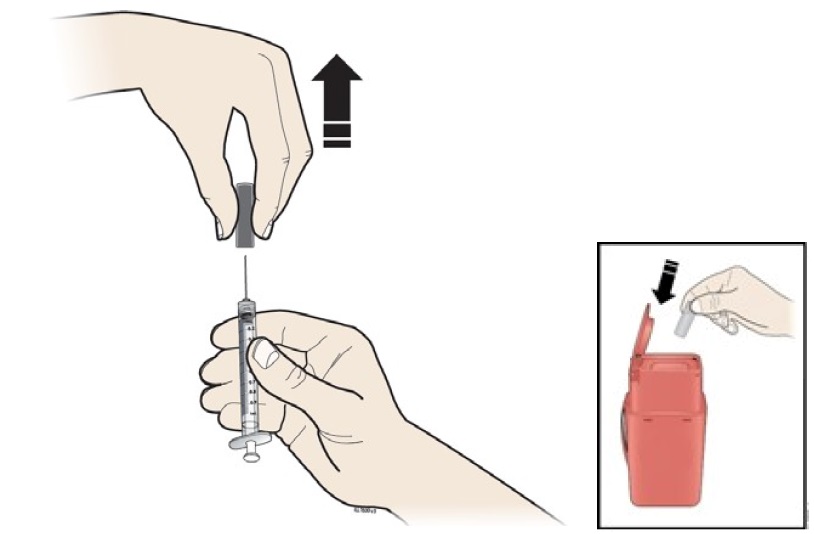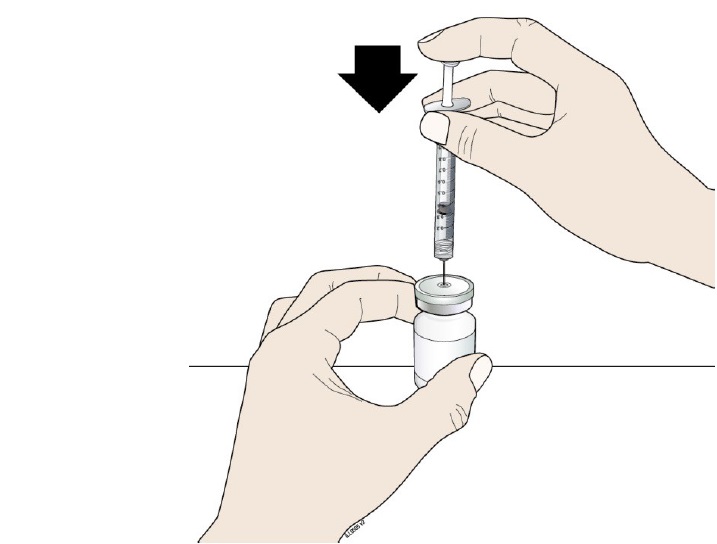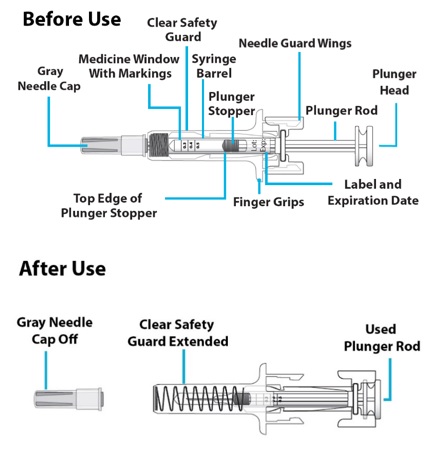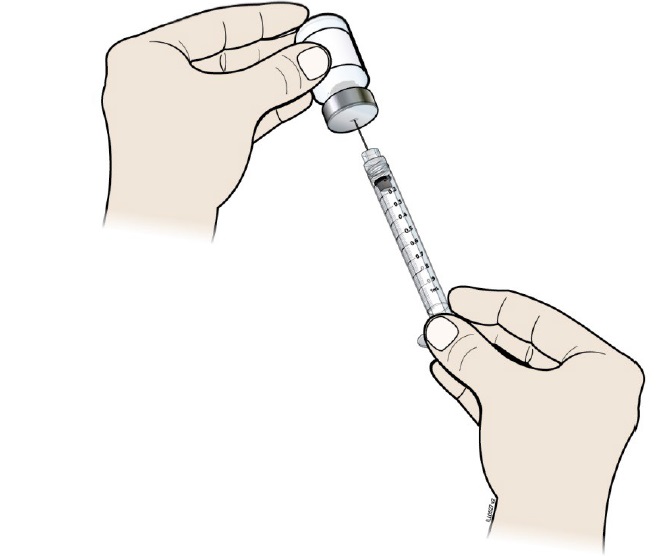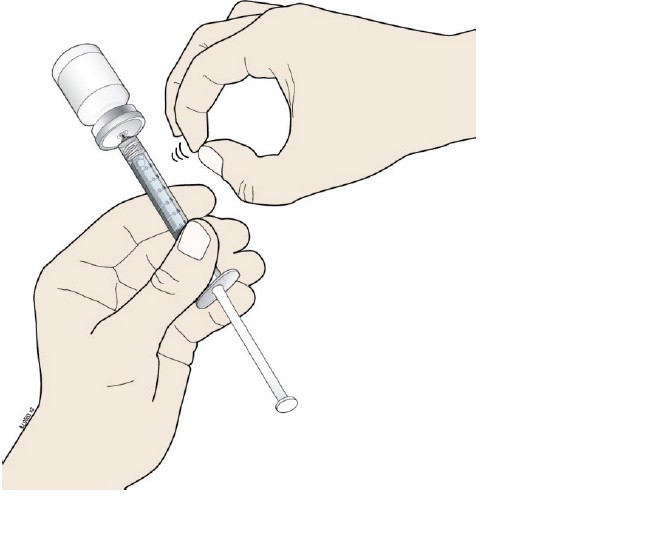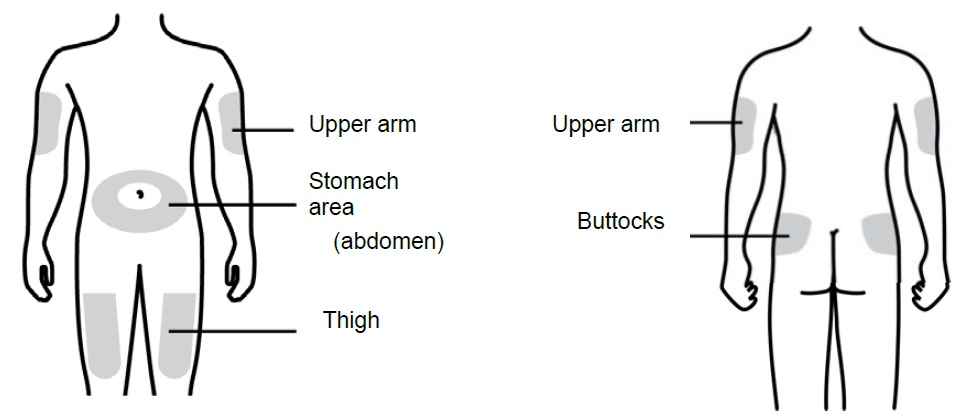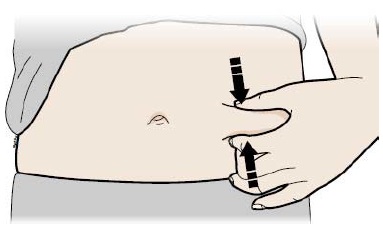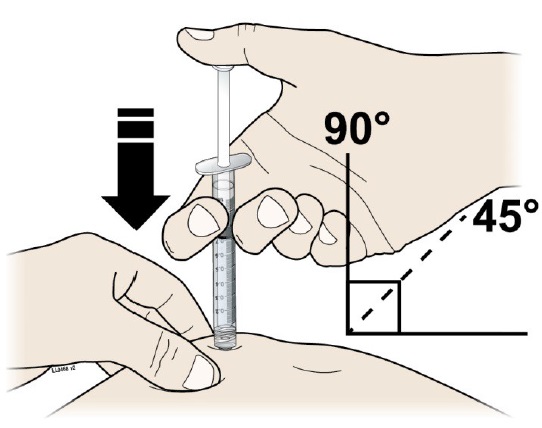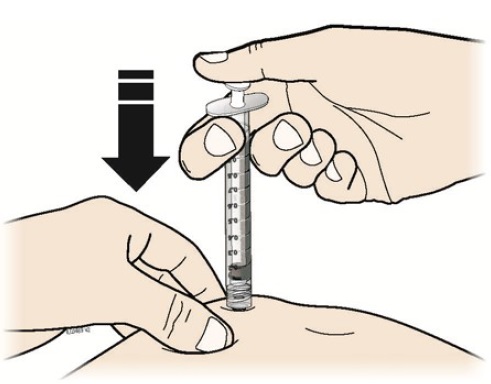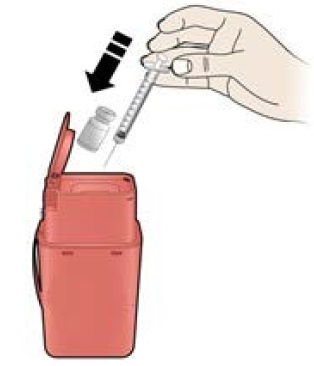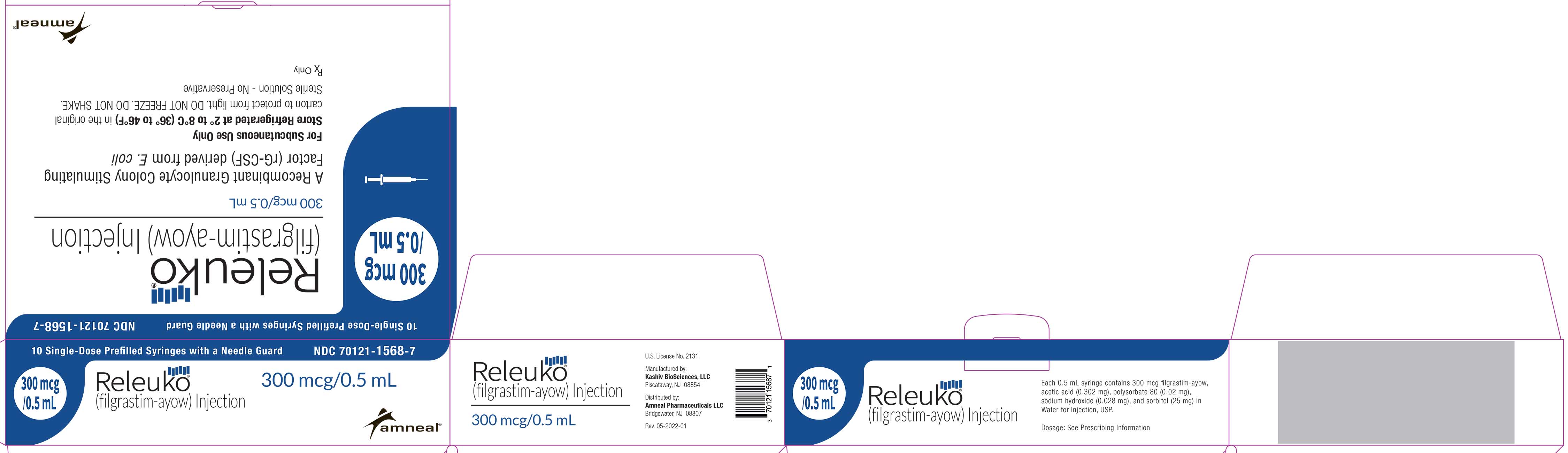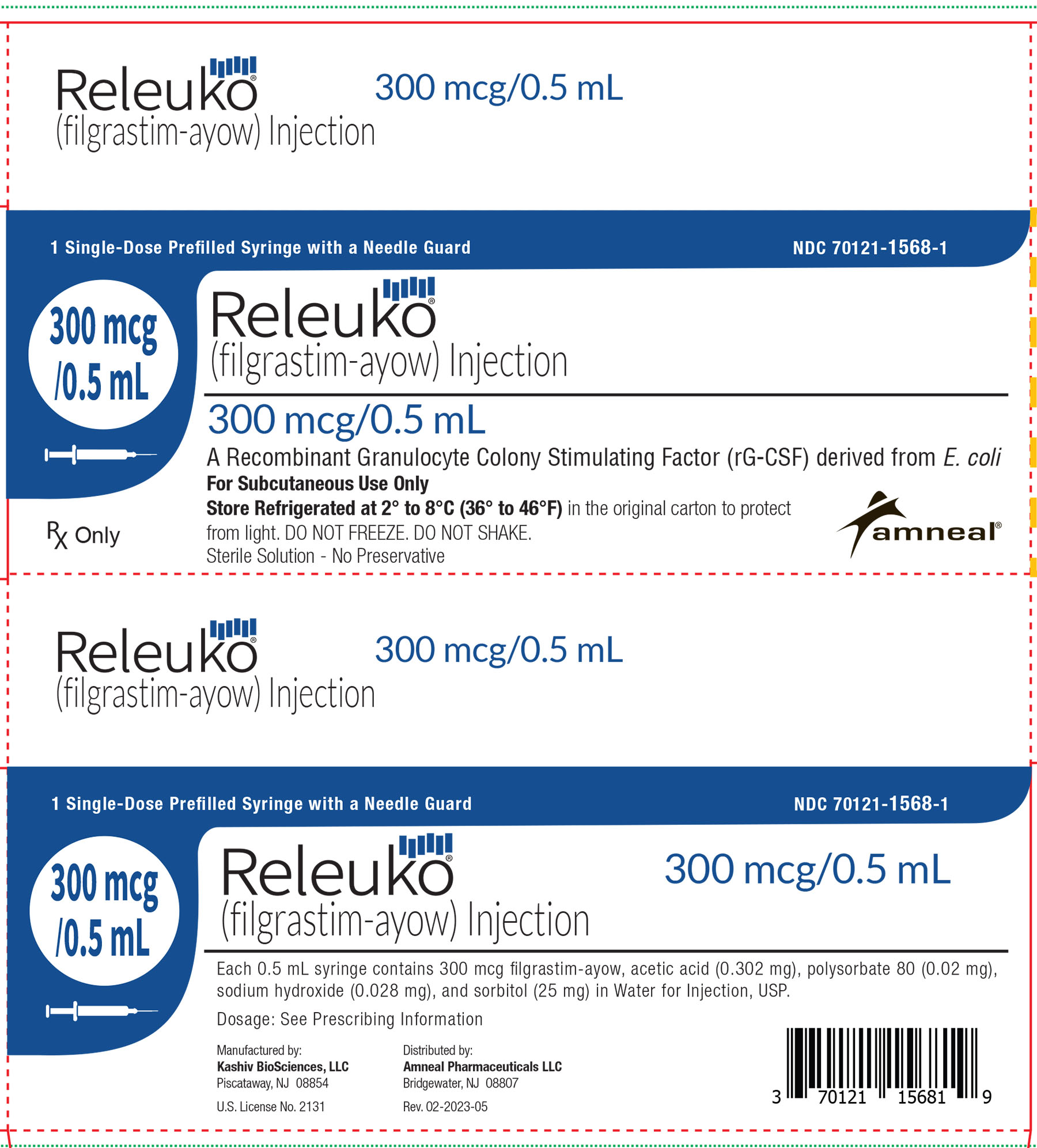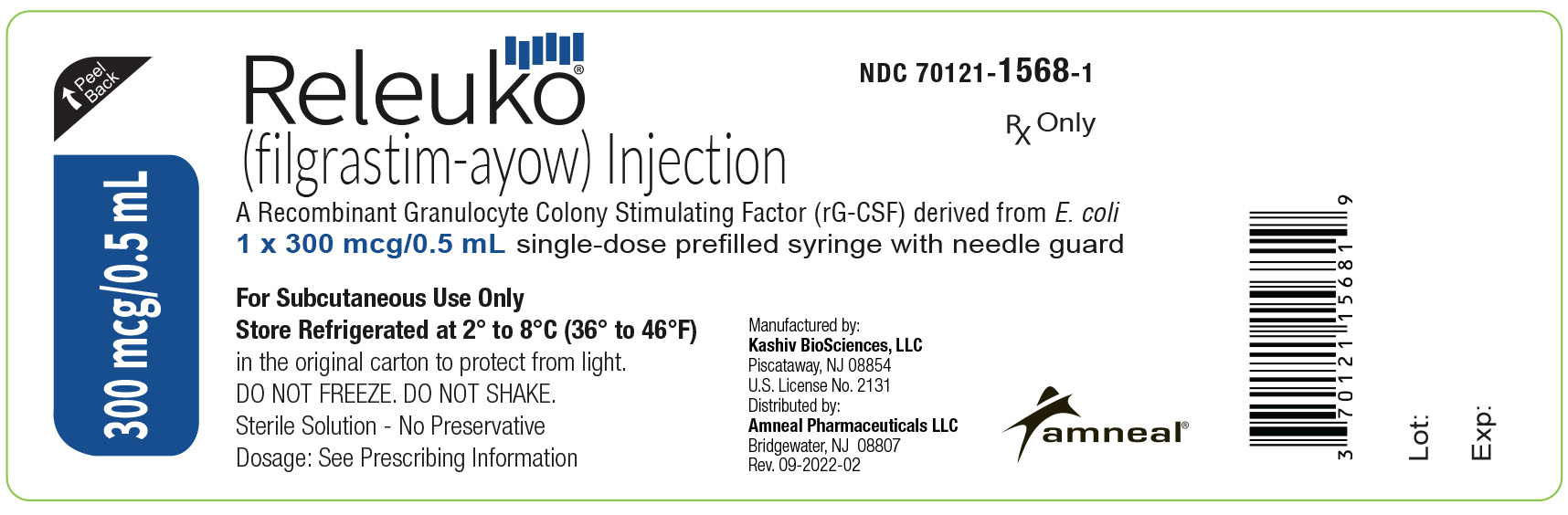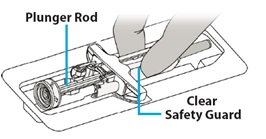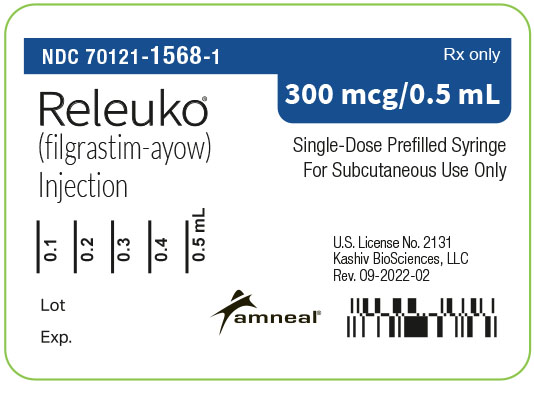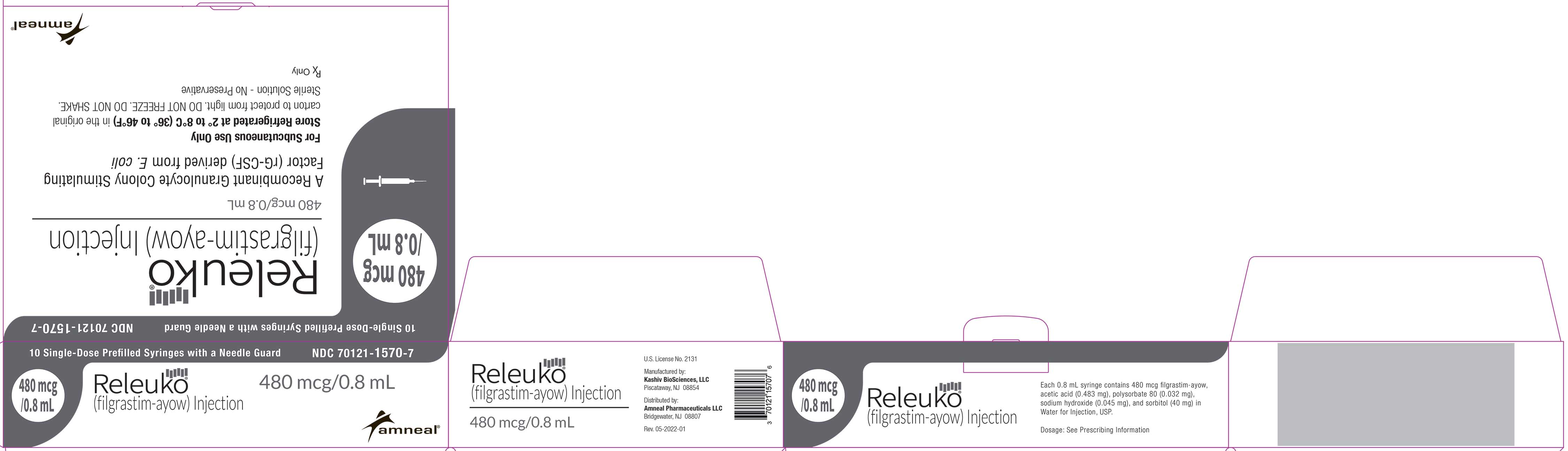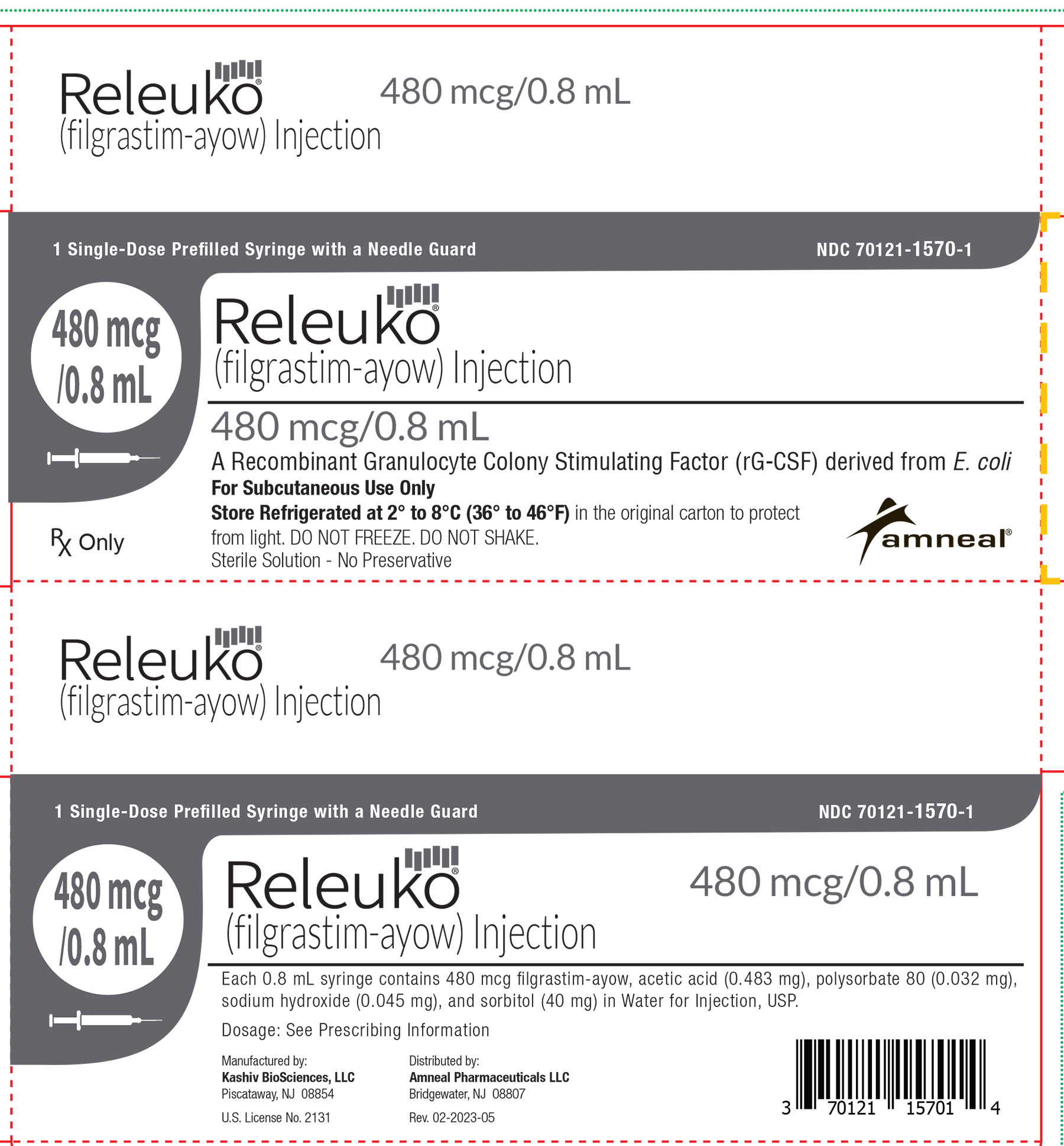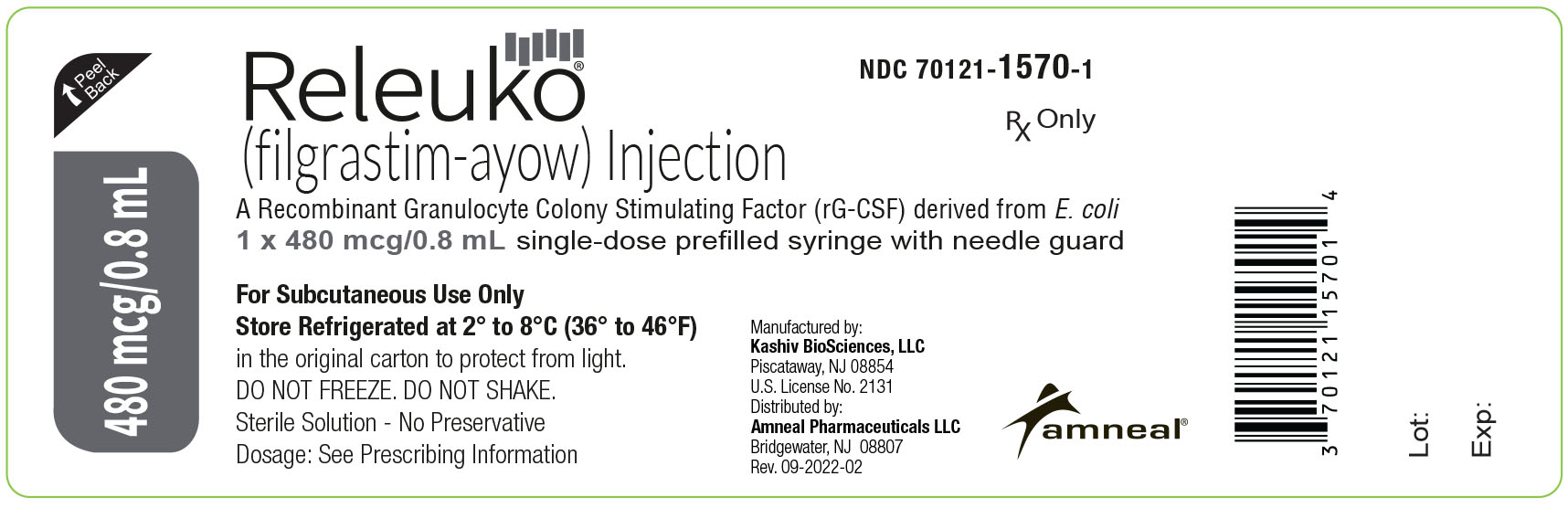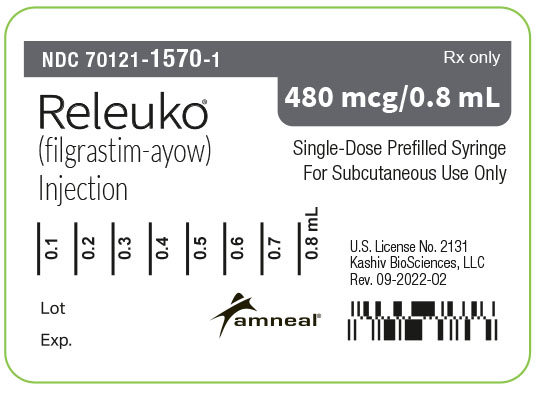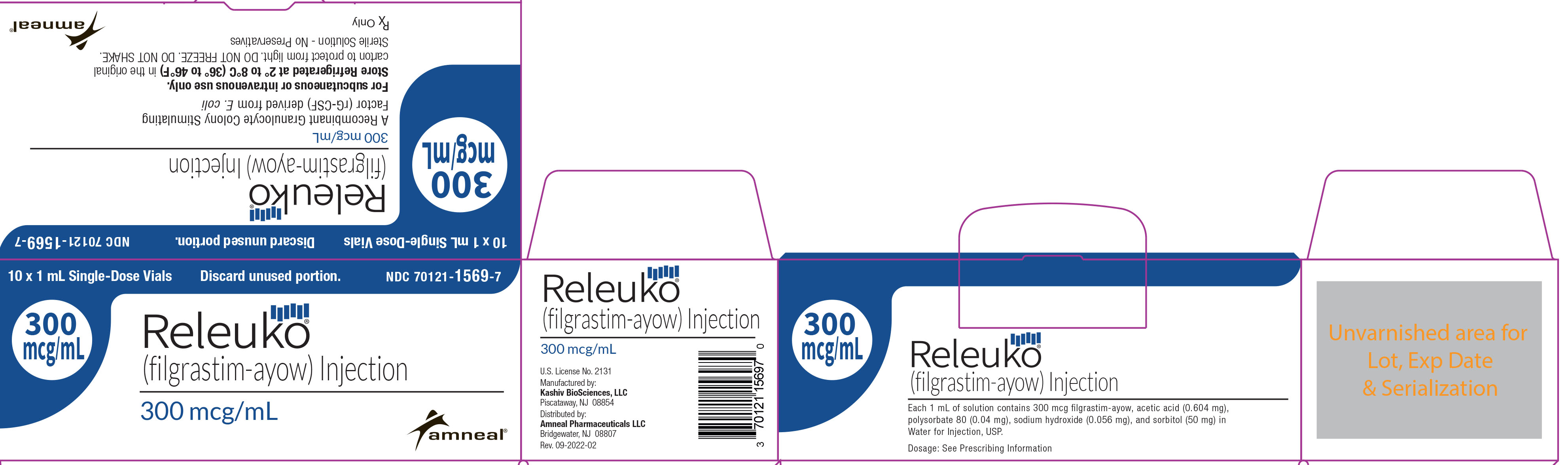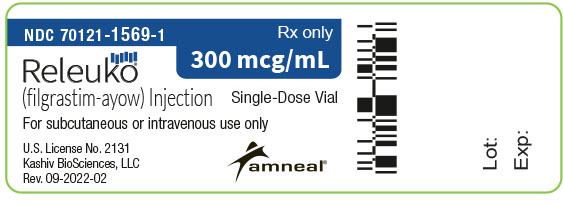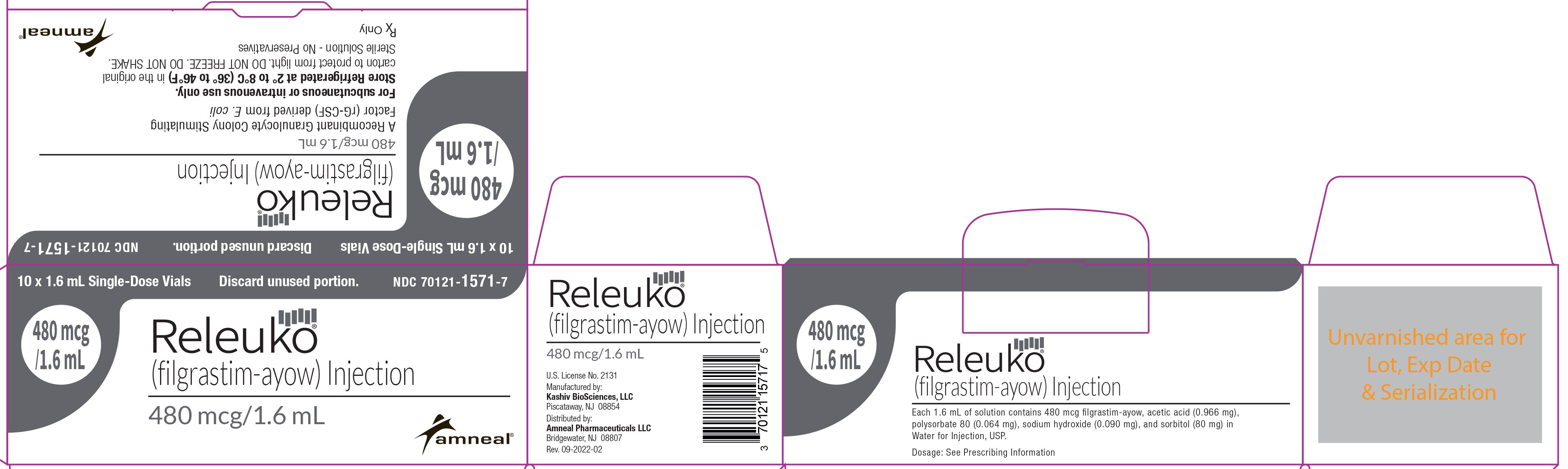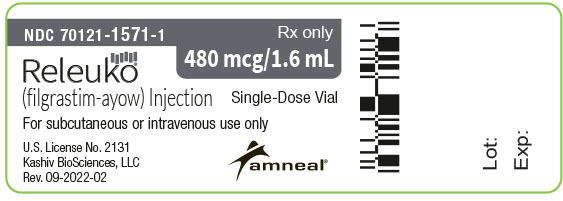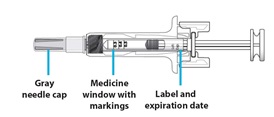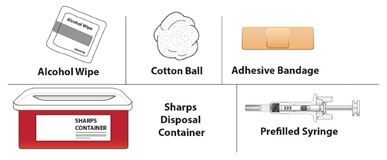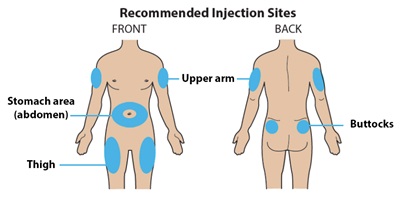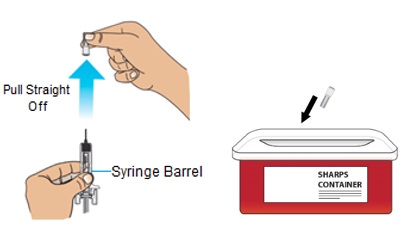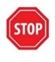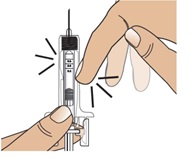 DRUG LABEL: RELEUKO
NDC: 70121-1568 | Form: INJECTION, SOLUTION
Manufacturer: Amneal Pharmaceuticals LLC
Category: prescription | Type: HUMAN PRESCRIPTION DRUG LABEL
Date: 20250424

ACTIVE INGREDIENTS: FILGRASTIM 300 ug/0.5 mL
INACTIVE INGREDIENTS: ACETIC ACID 0.302 mg/0.5 mL; SORBITOL 25 mg/0.5 mL; POLYSORBATE 80 0.02 mg/0.5 mL; SODIUM HYDROXIDE 0.028 mg/0.5 mL; WATER

HIGHLIGHTS OF PRESCRIBING INFORMATION

These highlights do not include all the information needed to use RELEUKO safely and effectively. See full prescribing information for RELEUKO.
RELEUKO® (filgrastim-ayow) injection, for subcutaneous or intravenous use.
Initial U.S. Approval: 2022
RELEUKO (filgrastim-ayow) is biosimilar* to NEUPOGEN® (filgrastim)

RECENT MAJOR CHANGES

Indications and Usage (1.4, 1.6) 04/2025

Dosage and Administration (2.3, 2.5) 04/2025

Warnings and Precautions (5.10, 5.12) 04/2025

1 INDICATIONS AND USAGE

RELEUKO is a leukocyte growth factor indicated to:

- Decrease the incidence of infection‚ as manifested by febrile neutropenia‚ in patients with nonmyeloid malignancies receiving myelosuppressive anti- cancer drugs associated with a significant incidence of severe neutropenia with fever. (1.1)
- Reduce the time to neutrophil recovery and the duration of fever, following induction or consolidation chemotherapy treatment of patients with acute myeloid leukemia (AML). (1.2)
- Reduce the duration of neutropenia and neutropenia-related clinical sequelae‚ e.g.‚ febrile neutropenia, in patients with nonmyeloid malignancies undergoing myeloablative chemotherapy followed by bone marrow transplantation (BMT). (1.3)
- Mobilize autologous hematopoietic progenitor cells into the peripheral blood for collection by leukapheresis (1.4)
- Reduce the incidence and duration of sequelae of severe neutropenia (e.g., fever‚ infections‚ oropharyngeal ulcers) in symptomatic patients with congenital neutropenia‚ cyclic neutropenia‚ or idiopathic neutropenia. (1.5)
- Increase survival in patients acutely exposed to myelosuppressive doses of radiation (Hematopoietic Syndrome of Acute Radiation Syndrome) (1.6)

2 DOSAGE AND ADMINISTRATION

- Patients with cancer receiving myelosuppressive chemotherapy or induction and/or consolidation chemotherapy for AML.

- Recommended starting dose is 5 mcg/kg/day subcutaneous injection, short intravenous infusion (15 to 30 minutes), or continuous intravenous infusion. See Full Prescribing Information for recommended dosage adjustments and timing of administration (2.1)

- Patients with cancer undergoing bone marrow transplantation
  - 10 mcg/kg/day given as an intravenous infusion no longer than 24 hours. See Full Prescribing Information for recommended dosage adjustments and timing of administration. (2.2)
- Patients undergoing autologous peripheral blood progenitor cell collection and therapy
  - 10 mcg/kg/day subcutaneous injection (2.3)
  - Administer for at least 4 days before first leukapheresis procedure and continue until last leukapheresis (2.3)
- Patients with congenital neutropenia
  - Recommended starting dose is 6 mcg/kg subcutaneous injection twice daily (2.4)
- Patients with cyclic or idiopathic neutropenia
  - Recommended starting dose is 5 mcg/kg subcutaneous injection daily (2.4)
- Patients acutely exposed to myelosuppressive doses of radiation
  - 10 mcg/kg/day subcutaneous injection (2.5)
- Direct administration of less than 0.3 mL (180 mcg) using RELEUKO prefilled syringe is not recommended due to potential for dosing errors. (2.6)

3 DOSAGE FORMS AND STRENGTHS

Vial

- Injection: 300 mcg/mL in a single-dose vial (3)
- Injection: 480 mcg/1.6 mL (300 mcg/mL) in a single-dose vial (3)

Prefilled Syringe

- Injection: 300 mcg/0.5 mL in a single-dose prefilled syringe (3)
- Injection: 480 mcg/0.8 mL in a single-dose prefilled syringe (3)

4 CONTRAINDICATIONS

Patients with a history of serious allergic reactions to human granulocyte colony-stimulating factors such as filgrastim products or pegfilgrastim products. (4)

5 WARNINGS AND PRECAUTIONS

- Fatal splenic rupture: Evaluate patients who report left upper abdominal or shoulder pain for an enlarged spleen or splenic rupture. (5.1)
- Acute respiratory distress syndrome (ARDS): Evaluate patients who develop fever and lung infiltrates or respiratory distress for ARDS. Discontinue RELEUKO in patients with ARDS. (5.2)
- Serious allergic reactions, including anaphylaxis: Permanently discontinue RELEUKO in patients with serious allergic reactions. (5.3)
- Fatal sickle cell crises: Discontinue RELEUKO if sickle cell crisis occurs. (5.4)
- Glomerulonephritis: Evaluate and consider dose-reduction or interruption of RELEUKO if causality is likely. (5.5)
- Myelodysplastic Syndrome (MDS) and Acute Myeloid Leukemia (AML): Monitor patients with breast and lung cancer using RELEUKO in conjunction with chemotherapy and/or radiotherapy for signs and symptoms of MDS/AML. (5.8)
- Thrombocytopenia: Monitor platelet counts. (5.9)
- Aortitis: Aortitis has been reported in patients receiving filgrastim products. Discontinue RELEUKO if aortitis is suspected. (5.15)

6 ADVERSE REACTIONS

Most common adverse reactions in patients: (6.1)

- With nonmyeloid malignancies receiving myelosuppressive anti-cancer drugs (≥ 5% difference in incidence compared to placebo) are pyrexia, pain, rash, cough, and dyspnea.
- With AML (≥ 2% difference in incidence) are pain, epistaxis and rash.
- With nonmyeloid malignancies undergoing myeloablative chemotherapy followed by BMT (≥ 5% difference in incidence) is rash.
- Undergoing peripheral blood progenitor cell mobilization and collection (≥ 5% incidence) are bone pain, pyrexia and headache.
- With severe chronic neutropenia (SCN) (≥ 5% difference in incidence) are pain, anemia, epistaxis, diarrhea, hypoesthesia and alopecia.

To report SUSPECTED ADVERSE REACTIONS, contact Amneal Pharmaceuticals LLC at 1-877-835 5472, option 3 or FDA at 1-800-FDA-1088 or www.fda.gov/medwatch.

* Biosimilar means that the biological product is approved based on data demonstrating that it is highly similar to an FDA-approved biological product, known as a reference product, and that there are no clinically meaningful differences between the biosimilar product and the reference product. Biosimilarity of RELEUKO® has been demonstrated for the condition(s) of use (e.g., indication(s), dosing regimen(s)), strength(s), dosage form(s), and route(s) of administration described in its Full Prescribing Information.

FULL PRESCRIBING INFORMATION

1 INDICATIONS AND USAGE

1.1 Patients with Cancer Receiving Myelosuppressive Chemotherapy

RELEUKO is indicated to decrease the incidence of infection‚ as manifested by febrile neutropenia‚ in patients with nonmyeloid malignancies receiving myelosuppressive anti-cancer drugs associated with a significant incidence of severe neutropenia with fever [see Clinical Studies (14.1)].

1.2 Patients with Acute Myeloid Leukemia Receiving Induction or Consolidation Chemotherapy

RELEUKO is indicated for reducing the time to neutrophil recovery and the duration of fever, following induction or consolidation chemotherapy treatment of patients with acute myeloid leukemia (AML) [see Clinical Studies (14.2)].

1.3 Patients with Cancer Undergoing Bone Marrow Transplantation

RELEUKO is indicated to reduce the duration of neutropenia and neutropenia-related clinical sequelae‚ e.g.‚ febrile neutropenia, in patients with nonmyeloid malignancies undergoing myeloablative chemotherapy followed by bone marrow transplantation [see Clinical Studies (14.3)].

1.4 Patients Undergoing Autologous Peripheral Blood Progenitor Cell Collection and Therapy

RELEUKO is indicated for the mobilization of autologous hematopoietic progenitor cells into the peripheral blood for collection by leukapheresis [see Clinical Studies (14.4)].

1.5 Patients with Severe Chronic Neutropenia

RELEUKO is indicated for chronic administration to reduce the incidence and duration of sequelae of neutropenia (e.g.‚ fever‚ infections‚ oropharyngeal ulcers) in symptomatic patients with congenital neutropenia‚ cyclic neutropenia‚ or idiopathic neutropenia [see Clinical Studies (14.5)].

1.6 Patients Acutely Exposed to Myelosuppressive Doses of Radiation (Hematopoietic Syndrome of Acute Radiation Syndrome)

RELEUKO is indicated to increase survival in patients acutely exposed to myelosuppressive doses of radiation [see Clinical Studies (14.6)].

2 DOSAGE AND ADMINISTRATION

2.1 Dosage in Patients with Cancer Receiving Myelosuppressive Chemotherapy or Induction and/or Consolidation Chemotherapy for AML

The recommended starting dosage of RELEUKO is 5 mcg/kg/day‚ administered as a single daily injection by subcutaneous injection‚ by short intravenous infusion (15 to 30 minutes)‚ or by continuous intravenous infusion. Obtain a complete blood count (CBC) and platelet count before instituting RELEUKO therapy and monitor twice weekly during therapy. Consider dose escalation in increments of 5 mcg/kg for each chemotherapy cycle‚ according to the duration and severity of the absolute neutrophil count (ANC) nadir. Recommend stopping RELEUKO if the ANC increases beyond 10‚000/mm^3 [see Warnings and Precautions (5.10)].

Administer RELEUKO at least 24 hours after cytotoxic chemotherapy. Do not administer RELEUKO within the 24- hour period prior to chemotherapy [see Warnings and Precautions (5.13)]. A transient increase in neutrophil count is typically seen 1 to 2 days after initiation of RELEUKO therapy. Therefore, to ensure a sustained therapeutic response administer RELEUKO daily for up to 2 weeks or until the ANC has reached 10‚000/mm^3 following the expected chemotherapy-induced neutrophil nadir. The duration of RELEUKO therapy needed to attenuate chemotherapy-induced neutropenia may be dependent on the myelosuppressive potential of the chemotherapy regimen employed.

2.2 Dosage in Patients with Cancer Undergoing Bone Marrow Transplantation

The recommended dosage of RELEUKO following bone marrow transplantation (BMT) is 10 mcg/kg/day given as an intravenous infusion no longer than 24 hours. Administer the first dose of RELEUKO at least 24 hours after cytotoxic chemotherapy and at least 24 hours after bone marrow infusion. Monitor CBCs and platelet counts frequently following marrow transplantation.

During the period of neutrophil recovery‚ titrate the daily dosage of RELEUKO against the neutrophil response (see Table 1).

Table 1. Recommended Dosage Adjustments During Neutrophil Recovery in Patients with Cancer Following BMT
Absolute Neutrophil Count | RELEUKO Dosage Adjustment
When ANC greater than 1,000/mm^3 for 3 consecutive days | Reduce to 5 mcg/kg/daya
Then, if ANC remains greater than 1,000/mm^3 for 3 more consecutive days | Discontinue RELEUKO
Then, if ANC decreases to less than 1,000/mm^3 | Resume at 5 mcg/kg/day

a If ANC decreases to less than 1,000/mm^3 at any time during the 5 mcg/kg/day administration‚ increase RELEUKO to 10 mcg/kg/day‚ and then follow the above steps.

2.3 Dosage in Patients Undergoing Autologous Peripheral Blood Progenitor Cell Collection and Therapy

The recommended dosage of RELEUKO for the mobilization of autologous peripheral blood progenitor cells (PBPC) is 10 mcg/kg/day given by subcutaneous injection. Administer RELEUKO for at least 4 days before the first leukapheresis procedure and continue until the last leukapheresis. Although the optimal duration of RELEUKO administration and leukapheresis schedule have not been established‚ administration of filgrastim for 6 to 7 days with leukaphereses on days 5‚ 6‚ and 7 was found to be safe and effective [see Clinical Studies (14.4)]. Monitor neutrophil counts after 4 days of RELEUKO‚ and discontinue RELEUKO if the white blood cell (WBC) count rises to greater than 100‚000/mm^3.

2.4 Dosage in Patients with Severe Chronic Neutropenia

Prior to starting RELEUKO in patients with suspected chronic neutropenia, confirm the diagnosis of severe chronic neutropenia (SCN) by evaluating serial CBCs with differential and platelet counts‚ and evaluating bone marrow morphology and karyotype. The use of RELEUKO prior to confirmation of a correct diagnosis of SCN may impair diagnostic efforts and may thus impair or delay evaluation and treatment of an underlying condition‚ other than SCN‚ causing the neutropenia.

The recommended starting dosage in patients with Congenital Neutropenia is 6 mcg/kg as a twice daily subcutaneous injection and the recommended starting dosage in patients with Idiopathic or Cyclic Neutropenia is 5 mcg/kg as a single daily subcutaneous injection.

Dosage Adjustments in Patients with Severe Chronic Neutropenia
Chronic daily administration is required to maintain clinical benefit. Individualize the dosage based on the patient’s clinical course as well as ANC. In the SCN postmarketing surveillance study, the reported median daily doses of filgrastim were: 6 mcg/kg (congenital neutropenia), 2.1 mcg/kg (cyclic neutropenia), and 1.2 mcg/kg (idiopathic neutropenia). In rare instances, patients with congenital neutropenia have required doses of filgrastim greater than or equal to 100 mcg/kg/day.

Monitor CBCs for Dosage Adjustments
During the initial 4 weeks of RELEUKO therapy and during the 2 weeks following any dosage adjustment‚ monitor CBCs with differential and platelet counts. Once a patient is clinically stable‚ monitor CBCs with differential and platelet counts monthly during the first year of treatment. Thereafter, if the patient is clinically stable, less frequent routine monitoring is recommended.

2.5 Dosage in Patients Acutely Exposed to Myelosuppressive Doses of Radiation (Hematopoietic Syndrome of Acute Radiation Syndrome)

The recommended dose of RELEUKO is 10 mcg/kg as a single daily subcutaneous injection for patients exposed to myelosuppressive doses of radiation. Administer RELEUKO as soon as possible after suspected or confirmed exposure to radiation doses greater than 2 gray (Gy).

Estimate a patient’s absorbed radiation dose (i.e., level of radiation exposure) based on information from

public health authorities, biodosimetry if available, or clinical findings such as time to onset of vomiting or lymphocyte depletion kinetics.

Obtain a baseline CBC and then serial CBCs approximately every third day until the ANC remains greater than 1,000/mm^3 for 3 consecutive CBCs. Do not delay administration of RELEUKO if a CBC is not readily available.

Continue administration of RELEUKO until the ANC remains greater than 1,000/mm^3 for 3 consecutive CBCs or exceeds 10,000/mm^3 after a radiation-induced nadir.

2.6 Important Administration Instructions

RELEUKO is supplied in single-dose vials (for subcutaneous use or intravenous infusion) and single-dose prefilled syringes (for subcutaneous use) [see Dosage Forms and Strengths (3)]. Prior to use‚ remove the vial or prefilled syringe from the refrigerator and allow RELEUKO to reach room temperature for a minimum of 30 minutes and a maximum of 24 hours. Discard any vial or prefilled syringe left at room temperature for greater than 24 hours. Parenteral drug products should be inspected visually for particulate matter and discoloration prior to administration, whenever solution and container permit (the solution is clear and colorless). Do not administer RELEUKO if particulates or discoloration are observed.

Discard unused portion of RELEUKO in vials or prefilled syringes; do not re-enter the vial. Do not save unused drug for later administration.

Subcutaneous Injection

Inject RELEUKO subcutaneously in the outer area of upper arms, abdomen, thighs, or upper outer areas of the buttock. If patients or caregivers are to administer RELEUKO, instruct them in appropriate injection technique and ask them to follow the subcutaneous injection procedures in the Instructions for Use for the vial or prefilled syringe [see Patient Counseling Information (17)].

Patient self-administration and administration by a caregiver may benefit from training by a healthcare professional. Training by the healthcare provider should aim to demonstrate to those patients and caregivers how to measure the dose of RELEUKO, and the focus should be on ensuring that a patient or caregiver can successfully perform all the steps in the Instructions for Use for the vial or prefilled syringe. If a patient or caregiver is not able to demonstrate that they can measure the dose and administer the product successfully, you should consider whether the patient is an appropriate candidate for self-administration of RELEUKO or whether the patient would benefit from a different RELEUKO presentation. If a patient or caregiver experiences difficulty measuring the required dose, especially if it is other than the entire contents of the RELEUKO prefilled syringe, use of the RELEUKO vial may be considered.

If the patient or caregiver misses a dose of RELEUKO, instruct them to contact their healthcare provider.

Administration Instructions for the Prefilled Syringe

The RELUEKO prefilled syringe with BD UltraSafe Plus™ Passive Needle Guard is not designed to allow for direct administration of doses of less than 0.3 mL (180 mcg). The spring-mechanism of the needle guard apparatus affixed to the prefilled syringe interferes with the visibility of the graduation markings on the syringe barrel corresponding to 0.1 mL and 0.2 mL. The visibility of these markings is necessary to accurately measure doses of RELEUKO less than 0.3 mL (180 mcg) for direct administration. Thus, the direct administration to patients requiring doses of less than 0.3 mL (180 mcg) is not recommended due to the potential for dosing errors. For direct administration of doses less than 0.3 mL (180 mcg) use RELUEKO single-dose vial.

Administration Instructions for Dilution (Vial Only)

If required for intravenous administration‚ RELEUKO (vial only) may be diluted in 5% Dextrose Injection, USP from a concentration of 300 mcg/mL to 5 mcg/mL (do not dilute to a final concentration less than 5 mcg/mL). RELEUKO diluted to concentrations from 5 mcg/mL to 15 mcg/mL should be protected from adsorption to plastic materials by the addition of Albumin (Human) to a final concentration of 2 mg/mL. When diluted in 5% Dextrose Injection, USP or 5% Dextrose plus Albumin (Human)‚ RELEUKO is compatible with glass bottles‚ polyvinyl chloride (PVC) and polyolefin intravenous bags‚ and polypropylene syringes. Do not dilute with saline at any time because the product may precipitate.

Diluted RELEUKO solution can be stored at room temperature for up to 4 hours. This 4-hour time period includes the time during room temperature storage of the infusion solution and the duration of the infusion.

3 DOSAGE FORMS AND STRENGTHS

RELEUKO is a clear, colorless, preservative-free solution available as:

Vial:

- Injection: 300 mcg/mL in a single-dose vial
- Injection: 480 mcg/1.6 mL (300 mcg/mL) in a single-dose vial

Prefilled Syringe:

- Injection: 300 mcg/0.5 mL in a single-dose prefilled syringe
- Injection: 480 mcg/0.8 mL in a single-dose prefilled syringe

4 CONTRAINDICATIONS

RELEUKO is contraindicated in patients with a history of serious allergic reactions to human granulocyte colony-stimulating factors such as filgrastim products or pegfilgrastim products [see Warnings and Precautions (5.3)].

5 WARNINGS AND PRECAUTIONS

5.1 Splenic Rupture

Splenic rupture, including fatal cases, has been reported following the administration of filgrastim products. Evaluate patients who report left upper abdominal or shoulder pain for an enlarged spleen or splenic rupture.

5.2 Acute Respiratory Distress Syndrome

Acute respiratory distress syndrome (ARDS) has been reported in patients receiving filgrastim products. Evaluate patients who develop fever and lung infiltrates or respiratory distress for ARDS. Discontinue RELEUKO in patients with ARDS.

5.3 Serious Allergic Reactions

Serious allergic reactions, including anaphylaxis, have been reported in patients receiving filgrastim products. The majority of reported events occurred upon initial exposure. Provide symptomatic treatment for allergic reactions. Allergic reactions, including anaphylaxis, in patients receiving filgrastim products can recur within days after the discontinuation of initial anti-allergic treatment. Permanently discontinue RELEUKO in patients with serious allergic reactions. RELEUKO is contraindicated in patients with a history of serious allergic reactions to human granulocyte colony-stimulating factors such as filgrastim products or pegfilgrastim products.

5.4 Sickle Cell Disorders

Severe and sometimes fatal sickle cell crises can occur in patients with sickle cell disorders receiving filgrastim products. Discontinue RELEUKO if sickle cell crisis occurs.

5.5 Glomerulonephritis

Glomerulonephritis has occurred in patients receiving filgrastim products. The diagnoses were based upon azotemia, hematuria (microscopic and macroscopic), proteinuria, and renal biopsy. Generally, events of glomerulonephritis resolved after dose-reduction or discontinuation of filgrastim products. If glomerulonephritis is suspected, evaluate for cause. If causality is likely, consider dose-reduction or interruption of RELEUKO.

5.6 Alveolar Hemorrhage and Hemoptysis

Alveolar hemorrhage manifesting as pulmonary infiltrates and hemoptysis requiring hospitalization have been reported in healthy donors treated with filgrastim products undergoing peripheral blood progenitor cell (PBPC) collection mobilization. Hemoptysis resolved with discontinuation of filgrastim products. The use of RELEUKO for PBPC mobilization in healthy donors is not an approved indication.

5.7 Capillary Leak Syndrome

Capillary leak syndrome (CLS) has been reported after G-CSF administration, including filgrastim products, and is characterized by hypotension, hypoalbuminemia, edema and hemoconcentration. Episodes vary in frequency, severity and may be life-threatening if treatment is delayed. Patients who develop symptoms of capillary leak syndrome should be closely monitored and receive standard symptomatic treatment, which may include a need for intensive care.

5.8 Myelodysplastic Syndrome (MDS) and Acute Myeloid Leukemia (AML)

Patients with Severe Chronic Neutropenia
Confirm the diagnosis of SCN before initiating RELEUKO therapy.

MDS and AML have been reported to occur in the natural history of congenital neutropenia without cytokine therapy. Cytogenetic abnormalities, transformation to MDS, and AML have also been observed in patients treated with filgrastim products for SCN. Based on available data including a postmarketing surveillance study, the risk of developing MDS and AML appears to be confined to the subset of patients with congenital neutropenia. Abnormal cytogenetics and MDS have been associated with the eventual development of myeloid leukemia. The effect of filgrastim products on the development of abnormal cytogenetics and the effect of continued filgrastim products administration in patients with abnormal cytogenetics or MDS are unknown. Monitor patients for signs and symptoms of MDS/AML in these settings. If a patient with SCN develops abnormal cytogenetics or myelodysplasia‚ the risks and benefits of continuing RELEUKO should be carefully considered.

Patients with Breast and Lung Cancer
MDS and AML have been associated with the use of filgrastim products in conjunction with chemotherapy and/or radiotherapy in patients with breast and lung cancer. Monitor patients for signs and symptoms of MDS/AML in these settings.

5.9 Thrombocytopenia

Thrombocytopenia has been reported in patients receiving filgrastim products. Monitor platelet counts.

5.10 Leukocytosis

Patients with Cancer Receiving Myelosuppressive Chemotherapy
White blood cell counts of 100‚000/mm^3 or greater were observed in approximately 2% of patients receiving filgrastim at dosages above 5 mcg/kg/day. In patients with cancer receiving RELEUKO as an adjunct to myelosuppressive chemotherapy‚ to avoid the potential risks of excessive leukocytosis‚ it is recommended that RELEUKO therapy be discontinued if the ANC surpasses 10‚000/mm^3 after the chemotherapy-induced ANC nadir has occurred. Monitor CBCs at least twice weekly during therapy. Dosages of RELEUKO that increase the ANC beyond 10‚000/mm^3 may not result in any additional clinical benefit. In patients with cancer receiving myelosuppressive chemotherapy‚ discontinuation of filgrastim therapy usually resulted in a 50% decrease in circulating neutrophils within 1 to 2 days‚ with a return to pretreatment levels in 1 to 7 days.

Peripheral Blood Progenitor Cell Collection and Therapy

During the period of administration of RELEUKO for PBPC mobilization in patients with cancer, discontinue RELEUKO if the leukocyte count rises to > 100,000/mm^3.

5.11 Cutaneous Vasculitis

Cutaneous vasculitis has been reported in patients treated with filgrastim products. In most cases‚ the severity of cutaneous vasculitis was moderate or severe. Most of the reports involved patients with SCN receiving long-term filgrastim therapy. Hold RELEUKO therapy in patients with cutaneous vasculitis. RELEUKO may be started at a reduced dose when the symptoms resolve and the ANC has decreased.

5.12 Potential Effect on Malignant Cells

RELEUKO is a growth factor that primarily stimulates neutrophils. The granulocyte colony-stimulating factor (G-CSF) receptor through which RELEUKO acts has also been found on tumor cell lines. The possibility that RELEUKO acts as a growth factor for any tumor type cannot be excluded. The safety of filgrastim products in chronic myeloid leukemia (CML) and myelodysplasia has not been established.

When RELEUKO is used to mobilize PBPC‚ tumor cells may be released from the marrow and subsequently collected in the leukapheresis product. The effect of reinfusion of tumor cells has not been well studied‚ and the limited data available are inconclusive.

5.13 Simultaneous Use with Chemotherapy and Radiation Therapy Not Recommended

The safety and efficacy of RELEUKO given simultaneously with cytotoxic chemotherapy have not been established. Because of the potential sensitivity of rapidly dividing myeloid cells to cytotoxic chemotherapy‚ do not use RELEUKO in the period 24 hours before through 24 hours after the administration of cytotoxic chemotherapy [see Dosage and Administration (2.2)].

The safety and efficacy of RELEUKO have not been evaluated in patients receiving concurrent radiation therapy. Avoid the simultaneous use of RELEUKO with chemotherapy and radiation therapy.

5.14 Nuclear Imaging

Increased hematopoietic activity of the bone marrow in response to growth factor therapy has been associated with transient positive bone-imaging changes. This should be considered when interpreting bone-imaging results.

5.15 Aortitis

Aortitis has been reported in patients receiving filgrastim products. It may occur as early as the first week after start of therapy. Manifestations may include generalized signs and symptoms such as fever, abdominal pain, malaise, back pain, and increased inflammatory markers (e.g., c-reactive protein and white blood cell count). Consider aortitis in patients who develop these signs and symptoms without known etiology. Discontinue RELEUKO if aortitis is suspected.

6 ADVERSE REACTIONS

The following serious adverse reactions are discussed in greater detail in other sections of the labeling:

- Splenic Rupture [see Warnings and Precautions (5.1)]
- Acute Respiratory Distress Syndrome [see Warnings and Precautions (5.2)]
- Serious Allergic Reactions [see Warnings and Precautions (5.3)]
- Sickle Cell Disorders [see Warnings and Precautions (5.4)]
- Glomerulonephritis [see Warnings and Precautions (5.5)]
- Alveolar Hemorrhage and Hemoptysis [see Warnings and Precautious (5.6)]
- Capillary Leak Syndrome [see Warnings and Precautions (5.7)]
- Myelodysplastic Syndrome [see Warnings and Precautions (5.8)]
- Acute Myeloid Leukemia [see Warnings and Precautions (5.8)]
- Thrombocytopenia [see Warnings and Precautions (5.9)]
- Leukocytosis [see Warnings and Precautions (5.10)]
- Cutaneous Vasculitis [see Warnings and Precautions (5.11)]
- Aortitis [see Warnings and Precautions (5.15)]

6.1 Clinical Trials Experience

Because clinical trials are conducted under widely varying conditions, adverse reaction rates observed in the clinical trials of a drug cannot be directly compared with rates in the clinical trials of another drug and may not reflect the rates observed in clinical practice.

Adverse Reactions in Patients with Cancer Receiving Myelosuppressive Chemotherapy
The following adverse reaction data in Table 2 are from three randomized, placebo-controlled studies in patients with:

- small cell lung cancer receiving standard dose chemotherapy with cyclophosphamide‚ doxorubicin‚ and etoposide (Study 1)
- small cell lung cancer receiving ifosfamide, doxorubicin‚ and etoposide (Study 2), and
- non-Hodgkin’s lymphoma (NHL) receiving doxorubicin, cyclophosphamide, vindesine, bleomycin, methylprednisolone, and methotrexate (“ACVBP”) or mitoxantrone, ifosfamide, mitoguazone, teniposide, methotrexate, folinic acid, methylprednisolone, and methotrexate (“VIM3”) (Study 3).

A total of 451 patients were randomized to receive subcutaneous filgrastim 230 mcg/m^2 (Study 1), 240 mcg/m^2 (Study 2) or 4 or 5 mcg/kg/day (Study 3) (n = 294) or placebo (n = 157). The patients in these studies were median age 61 (range 29 to 78) years and 64% were male. The ethnicity was 95% Caucasian, 4% African American, and 1% Asian.

Table 2. Adverse Reactions in Patients with Cancer Receiving Myelosuppressive Chemotherapy (With ≥ 5% Higher Incidence in Filgrastim Compared to Placebo)
System Organ Class Preferred Term | Filgrastim (N = 294) | Placebo (N = 157)
Blood and lymphatic system disorders
Thrombocytopenia | 38% | 29%
Gastrointestinal disorders
Nausea | 43% | 32%
General disorders and administration site conditions
Pyrexia | 48% | 29%
Chest pain | 13% | 6%
Pain | 12% | 6%
Fatigue | 20% | 10%
Musculoskeletal and connective tissue disorders
Back pain | 15% | 8%
Arthralgia | 9% | 2%
Bone pain | 11% | 6%
Pain in extremity [Percent difference (Filgrastim – Placebo) was 4%.] | 7% | 3%
Nervous system disorders
Dizziness | 14% | 3%
Respiratory, thoracic and mediastinal disorders
Cough | 14% | 8%
Dyspnea | 13% | 8%
Skin and subcutaneous tissue disorders
Rash | 14% | 5%
Investigations
Blood lactate dehydrogenase Increased | 6% | 1%
Blood alkaline phosphatase increased | 6% | 1%

Adverse events with ≥ 5% higher incidence in filgrastim patients compared to placebo and associated with the sequelae of the underlying malignancy or cytotoxic chemotherapy delivered included anemia, constipation, diarrhea, oral pain, vomiting, asthenia, malaise, edema peripheral, hemoglobin decreased, decreased appetite, oropharyngeal pain, and alopecia.

Adverse Reactions in Patients with Acute Myeloid Leukemia
Adverse reaction data below are from a randomized, double-blind, placebo-controlled study in patients with AML (Study 4) who received an induction chemotherapy regimen of intravenous daunorubicin days 1, 2, and 3; cytosine arabinoside days 1 to 7; and etoposide days 1 to 5 and up to 3 additional courses of therapy (induction 2, and consolidation 1, 2) of intravenous daunorubicin, cytosine arabinoside, and etoposide. The safety population included 518 patients randomized to receive either 5 mcg/kg/day filgrastim (n = 257) or placebo (n = 261). The median age was 54 (range 16 to 89) years and 54% were male.

Adverse reactions with ≥ 2% higher incidence in filgrastim patients compared to placebo included epistaxis, back pain, pain in extremity, erythema, and rash maculo-papular.

Adverse events with ≥ 2% higher incidence in filgrastim patients compared to placebo and associated with the sequelae of the underlying malignancy or cytotoxic chemotherapy included diarrhea, constipation, and transfusion reaction.

Adverse Reactions in Patients with Cancer Undergoing Bone Marrow Transplantation
The following adverse reaction data are from one randomized, no treatment-controlled study in patients with acute lymphoblastic leukemia or lymphoblastic lymphoma receiving high-dose chemotherapy (cyclophosphamide or cytarabine, and melphalan) and total body irradiation (Study 5) and one randomized, no treatment-controlled study in patients with Hodgkin's disease (HD) and NHL undergoing high-dose chemotherapy and autologous bone marrow transplantation (Study 6). Patients receiving autologous bone marrow transplantation only were included in the analysis. A total of 100 patients received either 30 mcg/kg/day as a 4-hour infusion (Study 5) or 10 mcg/kg/day or 30 mcg/kg/day as a 24-hour infusion (Study 6) filgrastim (n = 72), no treatment control or placebo (n = 28). The median age was 30 (range 15 to 57) years, 57% were male.

Adverse reactions with ≥ 5% higher incidence in filgrastim patients compared to patients receiving no filgrastim included rash and hypersensitivity.

Adverse reactions in patients receiving intensive chemotherapy followed by autologous BMT with ≥ 5% higher incidence in filgrastim patients compared to patients receiving no filgrastim included thrombocytopenia, anemia, hypertension, sepsis, bronchitis, and insomnia.

Adverse Reactions in Patients with Cancer Undergoing Autologous Peripheral Blood Progenitor Cell Collection

The adverse reaction data in Table 3 are from a series of 7 trials in patients with cancer undergoing mobilization of autologous peripheral blood progenitor cells for collection by leukapheresis. Patients (n = 166) in all these trials underwent a similar mobilization/collection regimen: Filgrastim was administered for 6 to 8 days‚ in most cases the apheresis procedure occurred on days 5‚ 6, and 7. The dosage of filgrastim ranged between 5 to 30 mcg/kg/day and was administered subcutaneously by injection or continuous infusion. The median age was 39 (range 15 to 67) years, and 48% were male.

Table 3. Adverse Reactions in Patients with Cancer Undergoing Autologous PBPC in the Mobilization Phase (≥ 5% Incidence in Filgrastim Patients)

System Organ Class Preferred Term | Mobilization Phase; (N = 166)
Musculoskeletal and connective tissue disorders
Bone pain | 30%
General disorders and administration site conditions
Pyrexia | 16%
Investigations
Blood alkaline phosphatase increased | 11%
Nervous system disorders
Headache | 10%

Adverse Reactions in Patients with Severe Chronic Neutropenia

The following adverse reaction data were identified in a randomized, controlled study in patients with SCN receiving filgrastim (Study 7). 123 patients were randomized to a 4-month observation period followed by subcutaneous filgrastim treatment or immediate subcutaneous filgrastim treatment. The median age was 12 years (range 7 months to 76 years) and 46% were male. The dosage of filgrastim was determined by the category of neutropenia.

Initial dosage of filgrastim:

- Idiopathic neutropenia: 3.6 mcg/kg/day
- Cyclic neutropenia: 6 mcg/kg/day
- Congenital neutropenia: 6 mcg/kg/day divided 2 times per day

The dosage was increased incrementally to 12 mcg/kg/day divided 2 times per day if there was no response.

Adverse reactions with ≥ 5% higher incidence in filgrastim patients compared to patients receiving no filgrastim included arthralgia, bone pain, back pain, muscle spasms, musculoskeletal pain, pain in extremity, splenomegaly, anemia, upper respiratory tract infection, and urinary tract infection (upper respiratory tract infection and urinary tract infection were higher in the filgrastim arm, total infection related events were lower in filgrastim-treated patients), epistaxis, chest pain, diarrhea, hypoesthesia, and alopecia.

6.2 Postmarketing Experience

The following adverse reactions have been identified during post-approval use of filgrastim products. Because these reactions are reported voluntarily from a population of uncertain size, it is not always possible to reliably estimate their frequency or establish a causal relationship to drug exposure.

- splenic rupture and splenomegaly (enlarged spleen) [see Warnings and Precautions (5.1)]
- acute respiratory distress syndrome [see Warnings and Precautions (5.2)]
- anaphylaxis [see Warnings and Precautions (5.3)]
- sickle cell disorders [see Warnings and Precautions (5.4)]
- glomerulonephritis [see Warnings and Precautions (5.5)]
- alveolar hemorrhage and hemoptysis [see Warnings and Precautious (5.6)]
- capillary leak syndrome [see Warnings and Precautions (5.7)]
- leukocytosis [see Warnings and Precautions (5.10)]
- cutaneous vasculitis [see Warnings and Precautions (5.11)]
- Sweet’s syndrome (acute febrile neutrophilic dermatosis)
- decreased bone density and osteoporosis in pediatric patients receiving chronic treatment with filgrastim products
- myelodysplastic syndrome (MDS) and acute myeloid leukemia (AML) in patients with breast and lung cancer receiving chemotherapy and/or radiotherapy [see Warnings and Precautions (5.8)]
- aortitis [see Warnings and Precautions (5.15)]
- extramedullary hematopoiesis

USE IN SPECIFIC POPULATIONS

8.1 Pregnancy

Risk Summary

Available data from published studies, including several observational studies of pregnancy outcomes in women exposed to filgrastim products and those who were unexposed, have not established an association with filgrastim product use during pregnancy and major birth defects, miscarriage, or adverse maternal or fetal outcomes (see Data). Reports in the scientific literature have described transplacental passage of filgrastim in pregnant women when administered ≤ 30 hours prior to preterm delivery (≤ 30 weeks gestation). In animal reproduction studies, effects of filgrastim on prenatal development have been studied in rats and rabbits. No malformations were observed in either species. No maternal or fetal effects were observed in pregnant rats at doses up to 58 times the human doses. Filgrastim has been shown to have adverse effects in pregnant rabbits at doses 2 to 10 times higher than the human doses (see Data).

The estimated background risk of major birth defects and miscarriage for the indicated population is unknown. All pregnancies have a background risk of birth defect, loss, or other adverse outcomes. In the U.S. general population, the estimated background risks of major birth defects and miscarriage in clinically recognized pregnancies is 2 to 4% and 15 to 20%, respectively.

Data

Human Data

Several observational studies based on the Severe Chronic Neutropenia International Registry (SCNIR) described pregnancy outcomes in women with severe chronic neutropenia (SCN) who were exposed to filgrastim products during pregnancy and women with SCN who were unexposed. No major differences were seen between treated and untreated women with respect to pregnancy outcome (including miscarriage and preterm labor), newborn complications (including birth weight), and infections. Methodological limitations of these studies include small sample size and lack of generalizability due to the underlying maternal condition.

Animal Data
Effects of filgrastim on prenatal development have been studied in rats and rabbits. No malformations were observed in either species. Filgrastim has been shown to have adverse effects in pregnant rabbits at doses 2 to 10 times higher than the human doses. In pregnant rabbits showing signs of maternal toxicity, reduced embryo-fetal survival (at 20 and 80 mcg/kg/day) and increased abortions (at 80 mcg/kg/day) were observed. In pregnant rats, no maternal or fetal effects were observed at doses up to 575 mcg/kg/day, which is approximately 58 times higher than the human dose of 10 mcg/kg/day.

Offspring of rats administered filgrastim during the peri-natal and lactation periods exhibited a delay in external differentiation and growth retardation (≥ 20 mcg/kg/day) and slightly reduced survival rate (100 mcg/kg/day).

8.2 Lactation

Risk Summary
There is published literature documenting transfer of filgrastim into human milk. There are a few case reports describing the use of filgrastim in breastfeeding mothers with no adverse effects noted in the infants. There are no data on the effects of filgrastim products on milk production. Other filgrastim products are secreted poorly into breast milk, and filgrastim products are not absorbed orally by neonates. The developmental and health benefits of breastfeeding should be considered along with the mother’s clinical need for RELEUKO and any potential adverse effects on the breastfed child from RELEUKO or from the underlying maternal condition.

8.4 Pediatric Use

RELEUKO prefilled syringe with BD UltraSafe Plus™ Passive Needle Guard may not accurately measure volumes less than 0.3 mL due to the needle spring mechanism design. Therefore, the direct administration of a volume less than 0.3 mL using RELEUKO prefilled syringe is not recommended due to the potential for dosing errors. For direct administration of doses less than 0.3 mL (180 mcg) use RELEUKO single-dose vial.

In patients with cancer receiving myelosuppressive chemotherapy‚ 15 pediatric patients median age 2.6 (range 1.2 to 9.4) years with neuroblastoma were treated with myelosuppressive chemotherapy (cyclophosphamide‚ cisplatin‚ doxorubicin‚ and etoposide) followed by subcutaneous filgrastim at doses of 5, 10, or 15 mcg/kg/day for 10 days (n = 5/dose) (Study 8). The pharmacokinetics of filgrastim in pediatric patients after chemotherapy are similar to those in adults receiving the same weight-normalized doses, suggesting no age-related differences in the pharmacokinetics of filgrastim. In this population‚ filgrastim was well tolerated. There was one report of palpable splenomegaly and one report of hepatosplenomegaly associated with filgrastim therapy; however‚ the only consistently reported adverse event was musculoskeletal pain‚ which is no different from the experience in the adult population.

The safety and effectiveness of RELEUKO have been established in pediatric patients with SCN [see Clinical Studies (14.5)]. In a phase 3 study (Study 7) to assess the safety and efficacy of filgrastim in the treatment of SCN, 123 patients with a median age of 12 years (range 7 months to 76 years) were studied. Of the 123 patients, 12 were infants (7 months to 2 years of age), 49 were children (2 to 12 years of age), and 9 were adolescents (12 to 16 years of age). Additional information is available from a SCN postmarketing surveillance study, which includes long-term follow-up of patients in the clinical studies and information from additional patients who entered directly into the postmarketing surveillance study. Of the 731 patients in the surveillance study, 429 were pediatric patients < 18 years of age (range 0.9 to 17) [see Indications and Usage (1.5), Dosage and Administration (2.6) and Clinical Studies (14.5)].

Long-term follow-up data from the postmarketing surveillance study suggest that height and weight are not adversely affected in patients who received up to 5 years of filgrastim treatment. Limited data from patients who were followed in the phase 3 study for 1.5 years did not suggest alterations in sexual maturation or endocrine function.

Pediatric patients with congenital types of neutropenia (Kostmann’s syndrome, congenital agranulocytosis, or Schwachman-Diamond syndrome) have developed cytogenetic abnormalities and have undergone transformation to MDS and AML while receiving chronic filgrastim treatment. The relationship of these events to filgrastim product administration is unknown [see Warnings and Precautions (5.8) and Adverse Reactions (6)].

The use of RELEUKO to increase survival in pediatric patients acutely exposed to myelosuppressive doses of radiation is based on studies of filgrastim conducted in animals and clinical data supporting the use of filgrastim in other approved indications [see Dosage and Administration (2.1 to 2.4) and Clinical Studies (14.6)].

8.5 Geriatric Use

Among 855 subjects enrolled in 3 randomized, placebo-controlled trials of filgrastim-treated patients receiving myelosuppressive chemotherapy, there were 232 subjects age 65 or older, and 22 subjects age 75 or older. No overall differences in safety or effectiveness were observed between these subjects and younger subjects.

Clinical studies of filgrastim in other approved indications (i.e., BMT recipients, PBPC mobilization, and SCN) did not include sufficient numbers of subjects aged 65 and older to determine whether elderly subjects respond differently from younger subjects.

10 OVERDOSAGE

The maximum tolerated dose of filgrastim products has not been determined. In filgrastim clinical trials of patients with cancer receiving myelosuppressive chemotherapy‚ WBC counts > 100‚000/mm^3 have been reported in less than 5% of patients‚ but were not associated with any reported adverse clinical effects. Patients in the BMT studies received up to 138 mcg/kg/day without toxic effects‚ although there was a flattening of the dose response curve above daily doses of greater than 10 mcg/kg/day.

11 DESCRIPTION

Filgrastim-ayow, a leukocyte growth factor, is a 175 amino acid human granulocyte colony-stimulating factor (G-CSF) manufactured by recombinant DNA technology. Filgrastim-ayow is produced by Escherichia coli (E coli) bacteria into which has been inserted the human granulocyte colony-stimulating factor gene. Filgrastim-ayow has a molecular weight of 18‚800 daltons. The protein has an amino acid sequence that is identical to the natural sequence predicted from human DNA sequence analysis‚ except for the addition of an N-terminal methionine necessary for expression in E coli. Because filgrastim-ayow is produced in E coli‚ the product is non-glycosylated and thus differs from G-CSF isolated from a human cell. Kanamycin, 50 mcg/mL is final concentration, is used during the fermentation step of the manufacturing process. Kanamycin is not detectable in the final product.

RELEUKO (filgrastim-ayow) injection is a sterile‚ clear‚ colorless‚ preservative-free liquid containing filgrastim-ayow at a specific activity of 1.0 ± 0.6 x 10^8 U/mg (as measured by a cell mitogenesis assay). The product is available in single-dose vials for subcutaneous or intravenous use and prefilled syringes for subcutaneous use. The single-dose vials contain either 300 mcg/mL or 480 mcg/1.6 mL of filgrastim-ayow. The single-dose prefilled syringes contain either 300 mcg/0.5 mL or 480 mcg/0.8 mL of filgrastim-ayow. The RELEUKO drug product has a pH of 4.0. See table below for product composition of each single-dose vial or prefilled syringe.

 | 300 mcg/mL Vial | 480 mcg/1.6 mL Vial | 300 mcg/0.5 mL Syringe | 480 mcg / 0.8 mL Syringe
Filgrastim-ayow | 300 mcg | 480 mcg | 300 mcg | 480 mcg
Acetic acid | 0.604 mg | 0.966 mg | 0.302 mg | 0.483 mg
Polysorbate 80 | 0.04 mg | 0.064 mg | 0.02 mg | 0.032 mg
Sodium hydroxide | 0.056 mg | 0.090 mg | 0.028 mg | 0.045 mg
Sorbitol | 50 mg | 80 mg | 25 mg | 40 mg
Water for Injection,
USP q.s. ad [quantity sufficient to make.] | 1 mL | 1.6 mL | 0.5 mL | 0.8 mL

12 CLINICAL PHARMACOLOGY

12.1 Mechanism of Action

Colony-stimulating factors are glycoproteins which act on hematopoietic cells by binding to specific cell surface receptors and stimulating proliferation‚ differentiation commitment‚ and some end-cell functional activation.

Endogenous G-CSF is a lineage-specific colony-stimulating factor that is produced by monocytes‚ fibroblasts, and endothelial cells. G-CSF regulates the production of neutrophils within the bone marrow and affects neutrophil progenitor proliferation‚ differentiation, and selected end-cell functions (including enhanced phagocytic ability‚ priming of the cellular metabolism associated with respiratory burst‚ antibody-dependent killing, and the increased expression of some cell surface antigens). G-CSF is not species-specific and has been shown to have minimal direct in vivo or in vitro effects on the production or activity of hematopoietic cell types other than the neutrophil lineage.

12.2 Pharmacodynamics

In phase 1 studies involving 96 patients with various nonmyeloid malignancies‚ filgrastim administration resulted in a dose-dependent increase in circulating neutrophil counts over the dose range of 1 to 70 mcg/kg/day. This increase in neutrophil counts was observed whether filgrastim was administered intravenous (1 to 70 mcg/kg twice daily)‚ subcutaneous (1 to 3 mcg/kg once daily), or by continuous subcutaneous infusion (3 to 11 mcg/kg/day). With discontinuation of filgrastim therapy‚ neutrophil counts returned to baseline in most cases within 4 days. Isolated neutrophils displayed normal phagocytic (measured by zymosan-stimulated chemoluminescence) and chemotactic (measured by migration under agarose using N-formyl-methionyl-leucyl-phenylalanine [fMLP] as the chemotaxin) activity in vitro.

The absolute monocyte count was reported to increase in a dose-dependent manner in most patients receiving filgrastim; however‚ the percentage of monocytes in the differential count remained within the normal range. Absolute counts of both eosinophils and basophils did not change and were within the normal range following administration of filgrastim. Increases in lymphocyte counts following filgrastim administration have been reported in some normal subjects and patients with cancer.

White blood cell (WBC) differentials obtained during clinical trials have demonstrated a shift towards earlier granulocyte progenitor cells (left shift)‚ including the appearance of promyelocytes and myeloblasts‚ usually during neutrophil recovery following the chemotherapy-induced nadir. In addition‚ Dohle bodies‚ increased granulocyte granulation‚ and hypersegmented neutrophils have been observed. Such changes were transient and were not associated with clinical sequelae, nor were they necessarily associated with infection.

12.3 Pharmacokinetics

Filgrastim products exhibit nonlinear pharmacokinetics. Clearance is dependent on filgrastim product concentration and neutrophil count: G-CSF receptor-mediated clearance is saturated by high concentration of filgrastim products and is diminished by neutropenia. In addition, filgrastim products are cleared by the kidney.

Subcutaneous administration of 3.45 mcg/kg and 11.5 mcg/kg of filgrastim resulted in maximum serum concentrations of 4 and 49 ng/mL‚ respectively‚ within 2 to 8 hours. After intravenous administration, the volume of distribution averaged 150 mL/kg and the elimination half-life was approximately 3.5 hours in both normal subjects and subjects with cancer. Clearance rates of filgrastim were approximately 0.5 to 0.7 mL/minute/kg. Single parenteral doses or daily intravenous doses‚ over a 14-day period‚ resulted in comparable half-lives. The half-lives were similar for intravenous administration (231 minutes‚ following doses of 34.5 mcg/kg) and for subcutaneous administration (210 minutes‚ following filgrastim dosages of 3.45 mcg/kg). Continuous 24-hour intravenous infusions of 20 mcg/kg over an 11 to 20-day period produced steady-state serum concentrations of filgrastim with no evidence of drug accumulation over the time period investigated. The absolute bioavailability of filgrastim after subcutaneous administration is 60% to 70%.

Specific Populations

Patients Acutely Exposed to Myelosuppressive Doses of Radiation

The pharmacokinetics of filgrastim products are not available in patients acutely exposed to myelosuppressive doses of radiation. Based on limited pharmacokinetics data in irradiated non-human primates, the area under the time-concentration curve (AUC), reflecting the exposure to filgrastim in non-human primates at 10 mcg/kg dose of filgrastim, appears to be similar to that in humans at 5 mcg/kg. Simulations conducted using the population pharmacokinetic model indicates that the exposures to filgrastim at a filgrastim dose of 10 mcg/kg in patients acutely exposed to myelosuppressive doses of radiation are expected to exceed the exposures at a dose of 10 mcg/kg in irradiated non-human primates.

Pediatric Patients

The pharmacokinetics of filgrastim in pediatric patients after chemotherapy are similar to those in adult patients receiving the same weight-normalized doses, suggesting no age-related differences in the pharmacokinetics of filgrastim products [see Use in Specific Populations (8.4)].

Renal Impairment

In a study with healthy volunteers, subjects with moderate renal impairment, and subjects with end-stage renal disease (n = 4 per group), higher serum concentrations were observed in subjects with end-stage renal disease. However, dose adjustment in patients with renal impairment is not necessary.

Hepatic Impairment

Pharmacokinetics and pharmacodynamics of filgrastim are similar between subjects with hepatic impairment and healthy subjects (n = 12/group). The study included 10 subjects with mild hepatic impairment (Child-Pugh Class A) and 2 subjects with moderate hepatic impairment (Child-Pugh Class B). Therefore, RELEUKO dose adjustment for patients with hepatic impairment is not necessary.

12.6 Immunogenicity

The observed incidence of anti-drug antibodies is highly dependent on the sensitivity and specificity of the assay. Differences in assay methods preclude meaningful comparisons of the incidence of anti-drug antibodies in the studies described below with the incidence of anti-drug antibodies in other studies, including those of
filgrastim or of other filgrastim products.

While available data suggest that a small proportion of patients developed binding antibodies to filgrastim products, the nature and specificity of these antibodies has not been adequately studied. In clinical studies using filgrastim, the incidence of antibodies binding to filgrastim was 3% (11/333). In these 11 patients, no evidence of a neutralizing response was observed using a cell based bioassay. Because of the low occurrence of anti-drug antibodies, the effect of these antibodies on the pharmacokinetics, pharmacodynamics, safety, and/or effectiveness of filgrastim products is unknown.

Cytopenias resulting from an antibody response to exogenous growth factors have been reported on rare occasions in patients treated with other recombinant growth factors.

13 NONCLINICAL TOXICOLOGY

13.1 Carcinogenesis, Mutagenesis, Impairment of Fertility

The carcinogenic potential of filgrastim products has not been studied. Filgrastim failed to induce bacterial gene mutations in either the presence or absence of a drug metabolizing enzyme system. Filgrastim had no observed effect on the fertility of male or female rats at doses up to 500 mcg/kg.

13.2 Animal Toxicology and Pharmacology

Filgrastim was administered to monkeys‚ dogs‚ hamsters‚ rats‚ and mice as part of a nonclinical toxicology program, which included studies up to 1-year duration.

In the repeated-dose studies‚ changes observed were attributable to the expected pharmacological actions of filgrastim (i.e.‚ dose-dependent increases in white blood cell counts‚ increased circulating segmented neutrophils‚ and increased myeloid:erythroid ratio in bone marrow). Histopathologic examination of the liver and spleen revealed evidence of ongoing extramedullary granulopoiesis, and dose-related increases in spleen weight were seen in all species. These changes all reversed after discontinuation of treatment.

14 CLINICAL STUDIES

14.1 Patients with Cancer Receiving Myelosuppressive Chemotherapy

The safety and efficacy of filgrastim to decrease the incidence of infection‚ as manifested by febrile neutropenia‚ in patients with nonmyeloid malignancies receiving myelosuppressive anti-cancer drugs were established in a randomized‚ double-blind‚ placebo-controlled trial conducted in patients with small cell lung cancer (Study 1).

In Study 1, patients received up to 6 cycles of intravenous chemotherapy including intravenous cyclophosphamide and doxorubicin on day 1; and etoposide on days 1, 2, and 3 of 21 day cycles. Patients were randomized to receive filgrastim (n = 99) at a dose of 230 mcg/m^2 (4 to 8 mcg/kg/day) or placebo (n = 111). Study drug was administered subcutaneously daily beginning on day 4, for a maximum of 14 days. A total of 210 patients were evaluable for efficacy and 207 were evaluable for safety. The demographic and disease characteristics were balanced between arms with a median age of 62 (range 31 to 80) years; 64% males; 89% Caucasian; 72% extensive disease and 28% limited disease.

The main efficacy endpoint was the incidence of febrile neutropenia. Febrile neutropenia was defined as an ANC < 1,000/mm^3 and temperature > 38.2°C. Treatment with filgrastim resulted in a clinically and statistically significant reduction in the incidence of infection‚ as manifested by febrile neutropenia, 40% for filgrastim-treated patients and 76% for placebo-treated patients (p < 0.001). There were also statistically significant reductions in the incidence and overall duration of infection manifested by febrile neutropenia; the incidence, severity and duration of severe neutropenia (ANC < 500/mm^3); the incidence and overall duration of hospital admissions; and the number of reported days of antibiotic use.

14.2 Patients with Acute Myeloid Leukemia Receiving Induction or Consolidation Chemotherapy

The safety and efficacy of filgrastim to reduce the time to neutrophil recovery and the duration of fever, following induction or consolidation chemotherapy treatment of patients with acute myeloid leukemia (AML) was established in a randomized, double-blind‚ placebo-controlled‚ multi-center trial in patients with newly diagnosed, de novo AML (Study 4).

In Study 4 the initial induction therapy consisted of intravenous daunorubicin days 1, 2, and 3; cytosine arabinoside days 1 to 7; and etoposide days 1 to 5. Patients were randomized to receive subcutaneous filgrastim (n = 259) at a dose of 5 mcg/kg/day or placebo (n = 262) from 24 hours after the last dose of chemotherapy until neutrophil recovery (ANC ≥ 1,000/mm^3 for 3 consecutive days or ≥ 10,000/mm^3 for 1 day) or for a maximum of 35 days. The demographic and disease characteristics were balanced between arms with a median age of 54 (range 16 to 89) years; 54% males; initial white blood cell count (65% - <25,000 /mm^3 and 27% > 100,000/mm^3); 29% unfavorable cytogenetics.

The main efficacy endpoint was median duration of severe neutropenia defined as neutrophil count < 500/mm^3. Treatment with filgrastim resulted in a clinically and statistically significant reduction in median number of days of severe neutropenia, filgrastim-treated patients 14 days, placebo-treated patients 19 days (p = 0.0001: difference of 5 days (95% CI: -6.0, -4.0)). There was a reduction in the median duration of intravenous antibiotic use, filgrastim- treated patients: 15 days versus placebo-treated patients: 18.5 days; a reduction in the median duration of hospitalization, filgrastim-treated patients: 20 days versus placebo-treated patients: 25 days.

There were no statistically significant differences between the filgrastim and the placebo groups in complete remission rate (69% - filgrastim, 68% - placebo), median time to progression of all randomized patients (165 days - filgrastim, 186 days - placebo), or median overall survival (380 days – filgrastim, 425 days – placebo).

14.3 Patients with Cancer Undergoing Bone Marrow Transplantation

The safety and efficacy of filgrastim to reduce the duration of neutropenia in patients with nonmyeloid malignancies undergoing myeloablative chemotherapy followed by autologous bone marrow transplantation was evaluated in 2 randomized controlled trials of patients with lymphoma (Study 6 and Study 9). The safety and efficacy of filgrastim to reduce the duration of neutropenia in patients undergoing myeloablative chemotherapy followed by allogeneic bone marrow transplantation was evaluated in a randomized placebo-controlled trial (Study 10).

In Study 6, patients with Hodgkin’s disease received a preparative regimen of intravenous cyclophosphamide, etoposide, and BCNU (“CVP”), and patients with non-Hodgkin’s lymphoma received intravenous BCNU, etoposide, cytosine arabinoside and melphalan (“BEAM”). There were 54 patients randomized 1:1:1 to control, filgrastim 10 mcg/kg/day, and filgrastim 30 mcg/kg/day as a 24-hour continuous infusion starting 24 hours after bone marrow infusion for a maximum of 28 days. The median age was 33 (range 17 to 57) years; 56% males; 69% Hodgkin’s disease and 31% non-Hodgkin’s lymphoma.

The main efficacy endpoint was duration of severe neutropenia ANC < 500/mm^3. A statistically significant reduction in the median number of days of severe neutropenia (ANC < 500/mm^3) occurred in the filgrastim - treated groups versus the control group (23 days in the control group‚ 11 days in the 10 mcg/kg/day group‚ and 14 days in the 30 mcg/kg/day group [11 days in the combined treatment groups‚ p = 0.004]).

In Study 9, patients with Hodgkin’s disease and non-Hodgkin’s lymphoma received a preparative regimen of intravenous cyclophosphamide, etoposide, and BCNU (“CVP”). There were 43 evaluable patients randomized to continuous subcutaneous infusion filgrastim 10 mcg/kg/day (n = 19), filgrastim 30 mcg/kg/day (n = 10) and no treatment (n = 14) starting the day after marrow infusion for a maximum of 28 days. The median age was 33 (range 17 to 56) years; 67% males; 28% Hodgkin’s disease and 72% non-Hodgkin’s lymphoma.

The main efficacy endpoint was duration of severe neutropenia. There was statistically significant reduction in the median number of days of severe neutropenia (ANC < 500/mm^3) in the filgrastim-treated groups versus the control group (21.5 days in the control group versus 10 days in the filgrastim-treated groups, p < 0.001). The number of days of febrile neutropenia was also reduced significantly in this study (13.5 days in the control group versus 5 days in the filgrastim-treated groups‚ p < 0.0001).

In Study 10, 70 patients scheduled to undergo bone marrow transplantation for multiple underlying conditions using multiple preparative regimens were randomized to receive filgrastim 300 mcg/m^2/day (n = 33) or placebo (n = 37) days 5 through 28 after marrow infusion. The median age was 18 (range 1 to 45) years, 56% males. The underlying disease was: 67% hematologic malignancy, 24% aplastic anemia, 9% other. A statistically significant reduction in the median number of days of severe neutropenia occurred in the treated group versus the control group (19 days in the control group and 15 days in the treatment group‚ p < 0.001) and time to recovery of ANC to ≥ 500/mm^3 (21 days in the control group and 16 days in the treatment group‚ p < 0.001).

14.4 Patients Undergoing Autologous Peripheral Blood Progenitor Cell Collection and Therapy

The safety and efficacy of filgrastim to mobilize autologous peripheral blood progenitor cells for collection by leukapheresis was supported by the experience in uncontrolled trials, and a randomized trial comparing hematopoietic stem cell rescue using filgrastim -mobilized autologous peripheral blood progenitor cells to autologous bone marrow (Study 11). Patients in all these trials underwent a similar mobilization/collection regimen: filgrastim was administered for 6 to 7 days‚ in most cases the apheresis procedure occurred on days 5‚ 6, and 7. The dose of filgrastim ranged between 10 to 24 mcg/kg/day and was administered subcutaneously by injection or continuous intravenous infusion.

Engraftment was evaluated in 64 patients who underwent transplantation using filgrastim -mobilized autologous hematopoietic progenitor cells in uncontrolled trials. Two of the 64 patients (3%) did not achieve the criteria for engraftment as defined by a platelet count ≥ 20‚000/mm3 by day 28. In clinical trials of filgrastim for the mobilization of hematopoietic progenitor cells‚ filgrastim was administered to patients at doses between 5 to 24 mcg/kg/day after reinfusion of the collected cells until a sustainable ANC (≥ 500/mm3) was reached. The rate of engraftment of these cells in the absence of filgrastim post transplantation has not been studied.

Study 11 was a randomized, unblinded study of patients with Hodgkin’s disease or non-Hodgkin’s lymphoma undergoing myeloablative chemotherapy‚ 27 patients received filgrastim-mobilized autologous hematopoietic progenitor cells and 31 patients received autologous bone marrow. Thepreparative regimen was intravenous BCNU, etoposide, cytosine arabinoside and melphalan (“BEAM”).

Patients received daily filgrastim 24 hours after stem cell infusion at a dose of 5 mcg/kg/day. The median age was 33 (range 1 to 59) years; 64% males; 57% Hodgkin’s disease and 43% non-Hodgkin’s lymphoma. The main efficacy endpoint was number of days of platelet transfusions. Patients randomized to filgrastim -mobilized autologous peripheral blood progenitor cells compared to autologous bone marrow had significantly fewer days of platelet transfusions (median 6 vs 10 days).

14.5 Patients with Severe Chronic Neutropenia

The safety and efficacy of filgrastim to reduce the incidence and duration of sequelae of neutropenia (that is fever‚ infections, oropharyngeal ulcers) in symptomatic adult and pediatric patients with congenital neutropenia‚ cyclic neutropenia‚ or idiopathic neutropenia was established in a randomized controlled trial conducted in patients with severe neutropenia (Study 7).

Patients eligible for Study 7 had a history of severe chronic neutropenia documented with an ANC < 500/mm^3 on three occasions during a 6-month period, or in patients with cyclic neutropenia 5 consecutive days of ANC < 500/mm^3 per cycle. In addition, patients must have experienced a clinically significant infection during the previous 12 months. Patients were randomized to a 4-month observation period followed by filgrastim treatment or immediate filgrastim treatment. The median age was 12 years (range 7 months to 76 years); 46% males; 34% idiopathic, 17% cyclic and 49% congenital neutropenia.

Filgrastim was administered subcutaneously. The dose of filgrastim was determined by the category of neutropenia.
Initial dose of filgrastim:

- Idiopathic neutropenia: 3.6 mcg/kg/day
- Cyclic neutropenia: 6 mcg/kg/day
- Congenital neutropenia: 6 mcg/kg/day divided 2 times per day

The dose was increased incrementally to 12 mcg/kg/day divided 2 times per day if there was no response.

The main efficacy endpoint was response to filgrastim treatment. ANC response from baseline (< 500/mm^3) was defined as follows:

- Complete response: median ANC > 1,500/mm^3
- Partial response: median ANC ≥ 500/mm^3 and ≤ 1,500/mm^3 with a minimum increase of 100%
- No response: median ANC < 500/mm^3

There were 112 of 123 patients who demonstrated a complete or partial response to filgrastim treatment.

Additional efficacy endpoints included a comparison between patients randomized to 4 months of observation and patients receiving filgrastim of the following parameters:

- incidence of infection
- incidence of fever
- duration of fever
- incidence, duration, and severity of oropharyngeal ulcers
- number of days of antibiotic use

The incidence for each of these 5 clinical parameters was lower in the filgrastim arm compared to the control arm for cohorts in each of the 3 major diagnostic categories. An analysis of variance showed no significant interaction between treatment and diagnosis‚ suggesting that efficacy did not differ substantially in the different diseases. Although filgrastim substantially reduced neutropenia in all patient groups‚ in patients with cyclic neutropenia‚ cycling persisted but the period of neutropenia was shortened to 1 day.

14.6 Patients Acutely Exposed to Myelosuppressive Doses of Radiation (Hematopoietic Syndrome of Acute Radiation Syndrome)

Efficacy studies of filgrastim products could not be conducted in humans with acute radiation syndrome for ethical and feasibility reasons. Approval of this indication was based on efficacy studies conducted in animals and data supporting the use of filgrastim for other approved indications [see Dosage and Administration (2.1 to 2.4)].

Because of the uncertainty associated with extrapolating animal efficacy data to humans, the selection of human dose for RELEUKO is aimed at providing exposures to filgrastim that exceed those observed in animal efficacy studies. The 10 mcg/kg daily dose is selected for humans exposed to myelosuppressive doses of radiation because the exposure associated with such a dose is expected to exceed the exposure associated with a 10 mcg/kg dose in non-human primates [see Clinical Pharmacology (12.3)]. The safety of filgrastim at a daily dose of 10 mcg/kg has been assessed on the basis of clinical experience in approved indications.

The efficacy of filgrastim was studied in a randomized, blinded, placebo-controlled study in a non-human primate model of radiation injury. The planned sample size was 62 animals, but the study was stopped at the interim analysis with 46 animals because efficacy was established. Rhesus macaques were randomized to a control (n = 22) or treated (n = 24) group. Animals were exposed to total body irradiation of 7.4 ± 0.15 Gy delivered at 0.8 ± 0.03 Gy/min, representing a dose that would be lethal in 50% of animals by 60 days of follow-up (LD50/60). Starting on day 1 after irradiation, animals received daily subcutaneous injections of placebo (5% dextrose in water) or filgrastim (10 mcg/kg/day). Blinded treatment was stopped when one of the following criteria was met: ANC ≥ 1,000/mm^3 for 3 consecutive days, or ANC ≥ 10,000/mm^3 for more than 2 consecutive days within study day 1 to 5, or ANC ≥ 10,000/mm^3 any time after study day 5. Animals received medical management consisting of intravenous fluids, antibiotics, blood transfusions, and other support as required.

Filgrastim significantly (at 0.023 level of significance) reduced 60-day mortality in the irradiated non-human primates: 21% mortality (5/24) in the filgrastim group compared to 59% mortality (13/22) in the control group.

16 HOW SUPPLIED/STORAGE AND HANDLING

RELEUKO (filgrastim-ayow) injection is a clear, colorless, preservative-free solution supplied as:

Vials

Single-dose vials containing 300 mcg/mL of filgrastim-ayow. Dispensing packs of 10 vials (NDC 70121-1569-7).

Single-dose vials containing 480 mcg/1.6 mL (300 mcg/mL) of filgrastim-ayow. Dispensing packs of 10 vials (NDC 70121-1571-7).

Prefilled Syringes

Single-dose, prefilled syringe with 27 gauge, 1/2 inch needle with an UltraSafe PlusTM Needle Guard, containing 300 mcg/0.5 mL of filgrastim-ayow.

- Carton of one single-dose prefilled syringe (NDC 70121-1568-1)
- Pack of 10 prefilled syringes (NDC 70121-1568-7).

Single-dose, prefilled syringe with 27 gauge, 1/2 inch needle with an UltraSafe PlusTM Needle Guard, containing 480 mcg/0.8 mL of filgrastim-ayow.

- Carton of one single-dose prefilled syringe (NDC 70121-1570-1)
- Pack of 10 prefilled syringes (NDC 70121-1570-7).

Store RELEUKO refrigerated at 2°C to 8°C (36°F to 46°F) in the original pack to protect from light. Do not leave RELEUKO in direct sunlight. DO NOT freeze RELEUKO. Avoid shaking. Transport via a pneumatic tube has not been studied.

17 PATIENT COUNSELING INFORMATION

Advise the patient to read the FDA-approved patient labeling (Patient Information and Instructions for Use). Review the steps for direct patient administration with patients and caregivers. Training by the healthcare provider should aim to ensure that patients and caregivers can successfully perform all of the steps in the Instructions for Use of RELEUKO vial and prefilled syringe, including showing the patient or caregiver how to measure the required dose, particularly if a patient is on a dose other than the entire prefilled syringe. If a patient or caregiver is not able to demonstrate that they can measure the dose and administer the product successfully, you should consider whether the patient is an appropriate candidate for self-administration of RELEUKO or whether the patient would benefit from a different RELEUKO presentation.

Advise patients of the following risks and potential risks with RELEUKO:

- Rupture or enlargement of the spleen may occur. Symptoms include left upper quadrant abdominal pain or left shoulder pain. Advise patients to report pain in these areas to their physician immediately [see Warnings and Precautions (5.1)].
- Dyspnea, with or without fever, progressing to Acute Respiratory Distress Syndrome, may occur. Advise patients to report dyspnea to their physician immediately [see Warnings and Precautions (5.2)].
- Serious allergic reactions may occur, which may be signaled by rash, facial edema, wheezing, dyspnea, hypotension, or tachycardia. Advise patients to seek immediate medical attention if signs or symptoms of hypersensitivity reaction occur [see Warnings and Precautions (5.3)].
- In patients with sickle cell disease, sickle cell crisis and death have occurred. Discuss potential risks and benefits for patients with sickle cell disease prior to the administration of human granulocyte colony-stimulating factors [see Warnings and Precautions (5.4)].
- Glomerulonephritis may occur. Symptoms include swelling of the face or ankles, dark colored urine or blood in the urine, or a decrease in urine production. Advise patients to report signs or symptoms of glomerulonephritis to their physician immediately [see Warnings and Precautions (5.5)].
- There may be an increased risk of Myelodysplastic Syndrome and/or Acute Myeloid Leukemia in patients with congenital neutropenia who receive filgrastim products and in patients with breast and lung cancer who receive filgrastim products in conjunction with chemotherapy and/or radiation therapy. Symptoms of MDS and AML may include tiredness, fever, and easy bruising or bleeding. Advise patients to report to their physician signs and symptoms of MDS/AML [see Warnings and Precautions (5.8)].
- Cutaneous vasculitis may occur, which may be signaled by purpura or erythema. Advise patients to report signs or symptoms of vasculitis to their physician immediately [see Warnings and Precautions (5.11)].
- Aortitis may occur. Symptoms may include fever, abdominal pain, malaise, back pain, and increased inflammatory markers. Advise patients to report signs and symptoms of aortitis to their physician immediately [see Warnings and Precautions (5.15)].

Advise patients acutely exposed to myelosuppressive doses of radiation (Hematopoietic Syndrome of Acute Radiation Syndrome) that efficacy studies of filgrastim products for this indication could not be conducted in humans for ethical and feasibility reasons and that, therefore, approval of this use was based on efficacy studies conducted in animals [see Clinical Studies (14.6)].

Instruct patients who self-administer RELEUKO using the prefilled syringe or single-dose vial of the:

- Importance of following the applicable Instructions for Use.
- Dangers of reusing needles, syringes, or unused portions of single-dose vials.
- Importance of following local requirements for proper disposal of used syringes, needles, and unused vials.
- Importance of informing the healthcare provider if difficulty occurs when measuring or administering partial contents of the RELEUKO prefilled syringe. If difficulty occurs, use of the RELEUKO vial may be considered.
- Difference in product concentration of the RELEUKO prefilled syringe in comparison to the RELEUKO vial. When switching patients from the RELEUKO prefilled syringe to the RELEUKO vial, or vice versa, ensure that patients understand the correct volume to be administered since the concentration of RELEUKO differs between the prefilled syringe and the vial.

Manufactured by:

Kashiv BioSciences, LLC

Piscataway, NJ 08854

US License Number 2131

Distributed by:

Amneal Pharmaceuticals LLC

Bridgewater, NJ 08807

Rev. 04-2025-05

PATIENT INFORMATION

RELEUKO® (reh-loo-koe)
(filgrastim-ayow)
injection

What is RELEUKO?
RELEUKO is a man-made form of granulocyte colony-stimulating factor (G-CSF). G-CSF is a substance produced by the body. It stimulates the growth of neutrophils, a type of white blood cell important in the body’s fight against infection.

Acute Radiation Syndrome: The effectiveness of filgrastim for this use was only studied in animals, because it could not be studied in people.

Do not take RELEUKO if you have had a serious allergic reaction to human G-CSFs such as filgrastim products or pegfilgrastim products.

Before you take RELEUKO, tell your healthcare provider about all of your medical conditions, including if you:

- have a sickle cell disorder.
- have kidney problems.
- are receiving radiation therapy.
- are pregnant or plan to become pregnant. It is not known if RELEUKO will harm your unborn baby.
- are breastfeeding or plan to breastfeed. It is not known if RELEUKO passes into your breast milk.

Tell your healthcare provider about all the medicines you take, including prescription and over-the-counter medicines, vitamins, and herbal supplements.

How will I receive RELEUKO?

- RELEUKO injections can be given by a healthcare provider by intravenous (IV) infusion or under your skin (subcutaneous injection). Your healthcare provider may decide subcutaneous injections can be given at home by you or your caregiver. If RELEUKO is given at home, see the detailed “Instructions for Use” that comes with your RELEUKO for information on how to prepare and inject a dose of RELEUKO.
- You and your caregiver should be shown how to prepare and inject RELEUKO before you use it, by your healthcare provider.
- Your healthcare provider will tell you how much RELEUKO to inject and when to inject it. Do not change your dose or stop RELEUKO unless your healthcare provider tells you to.
- You should not inject a dose of RELEUKO less than 0.3 mL (180 mcg) from a RELEUKO prefilled syringe. A dose less than 0.3 mL cannot be accurately measured using the RELEUKO prefilled syringe.
- If you are receiving RELEUKO because you are also receiving chemotherapy, your dose of RELEUKO should be injected at least 24 hours before or 24 hours after your dose of chemotherapy. Your healthcare provider will do blood tests to monitor your white blood cell count, and if necessary, adjust your RELEUKO dose.
- If you are receiving RELEUKO because you have been suddenly (acutely) exposed to an amount of radiation that can affect your bone marrow (Acute Radiation Syndrome), you will need to have blood tests about every 3 days during treatment with RELEUKO to check your white blood cell count.
- If you miss a dose of RELEUKO, talk to your healthcare provider about when you should give your next dose.

What are the possible side effects of RELEUKO?
RELEUKO may cause serious side effects, including:

- Spleen rupture. Your spleen may become enlarged and can rupture. A ruptured spleen can cause death. Call your healthcare provider right away if you have pain in the left upper stomach (abdomen) area or your left shoulder.
- A serious lung problem called acute respiratory distress syndrome (ARDS). Call your healthcare provider or get emergency medical help right away if you have shortness of breath with or without a fever, trouble breathing, or a fast rate of breathing.
- Serious allergic reactions. RELEUKO can cause serious allergic reactions. These reactions can cause a rash over your whole body, shortness of breath, wheezing, dizziness, swelling around your mouth or eyes, fast heart rate, and sweating. If you have any of these symptoms, stop using RELEUKO and call your healthcare provider or get emergency medical help right away.
- Sickle cell crises. You may have a serious sickle cell crisis, which could lead to death, if you have a sickle cell disorder and receive RELEUKO. Call your healthcare provider right away if you have symptoms of sickle cell crisis such as pain or difficulty breathing.
- Kidney injury (glomerulonephritis). RELEUKO can cause kidney injury. Call your healthcare provider right away if you develop any of the following symptoms:
  - swelling of your face or ankles
  - blood in your urine or dark colored urine
  - you urinate less than usual
- Capillary leak syndrome. RELEUKO can cause fluid to leak from blood vessels into your body’s tissues. This condition is called “Capillary Leak Syndrome” (CLS). CLS can quickly cause you to have symptoms that may become life-threatening. Get emergency medical help right away if you develop any of the following symptoms:
  - swelling or puffiness and are urinating less than usual
  - trouble breathing
  - swelling of your stomach area (abdomen) and feeling of fullness
  - dizziness or feeling faint
  - a general feeling of tiredness
- Myelodysplastic syndrome (MDS) and acute myeloid leukemia (AML).
  - RELEUKO may increase the risk of developing a precancerous condition called MDS or a type of blood cancer called AML in people who were born with low white blood cell counts (congenital neutropenia).
  - If you have breast cancer or lung cancer, when RELEUKO is used with chemotherapy and radiation therapy, or with radiation therapy only, you may have an increased risk of developing MDS or AML.
  - Symptoms of MDS and AML may include tiredness, fever, and easy bruising or bleeding.
  - Call your healthcare provider if you develop any of these symptoms during treatment with RELEUKO.
- Decreased platelet count (thrombocytopenia). Your healthcare provider will check your blood during treatment with RELEUKO. Tell your healthcare provider if you have unusual bleeding or bruising during treatment with RELEUKO. This could be a sign of decreased platelet counts, which may reduce the ability of your blood to clot.
- Increased white blood cell count (leukocytosis). Your healthcare provider will check your blood during treatment with RELEUKO.
- Inflammation of your blood vessels (cutaneous vasculitis). Tell your healthcare provider right away if you develop purple spots or redness of your skin.
- Inflammation of the aorta (aortitis). Inflammation of the aorta (the large blood vessel which transports blood from the heart to the body) has been reported in patients who received filgrastim products. Symptoms may include fever, abdominal pain, feeling tired, and back pain. Call your healthcare provider if you experience these symptoms.

The most common side effects experienced in patients receiving RELEUKO include:

- Patients with cancer receiving chemotherapy: fever, pain, rash, cough, and shortness of breath
- Patients with acute myeloid leukemia receiving chemotherapy: pain, nose bleed, and rash
- Patients with cancer receiving chemotherapy followed by bone marrow transplant: rash
- Patients who are having their own blood cells collected: bone pain, fever, and headache
- Patients with severe chronic neutropenia: pain, decreased red blood cells, nose bleed, diarrhea, reduced sensation, and hair loss

These are not all the possible side effects of RELEUKO. Call your healthcare provider for medical advice about side effects. You may report side effects to FDA at 1-800-FDA-1088.

How should I store RELEUKO?

- Store RELEUKO in the refrigerator between 36°F to 46°F (2°C to 8°C).
- Do not freeze.
- Keep RELEUKO in the original pack to protect from light or physical damage. Do not leave RELEUKO in direct sunlight.
- Do not shake RELEUKO.
- Take RELEUKO out of the refrigerator 30 minutes before use and allow it to reach room temperature before preparing an injection.
- Throw away (dispose of) any RELEUKO that has been left at room temperature for longer than 24 hours.
- After you inject your dose, throw away (dispose of) any unused RELEUKO left in the vials or prefilled syringes. Do not save unused RELEUKO in the vials or prefilled syringes for later use.

Keep RELEUKO and all medicines out of the reach of children.

General information about the safe and effective use of RELEUKO.
Medicines are sometimes prescribed for purposes other than those listed in a Patient Information leaflet. Do not use RELEUKO for a condition for which it was not prescribed. Do not give RELEUKO to other people, even if they have the same symptoms that you have. It may harm them. You can ask your pharmacist or healthcare provider for information about RELEUKO that is written for healthcare professionals.

What are the ingredients in RELEUKO?
Active ingredient: filgrastim-ayow
Inactive ingredients: acetic acid, polysorbate 80, sodium hydroxide, sorbitol and water for injection
Manufactured by: Kashiv BioSciences, LLC, Piscataway, NJ 08854
US License No. 2131
Distributed by: Amneal Pharmaceuticals LLC, Bridgewater, NJ, 08807
For more information go to www.Releuko.us or call 1-877-835-5472.

This Patient Information has been approved by the U.S. Food and Drug Administration .

Rev. 04-2025-03

Instructions for Use (PFS)

RELEUKO® (reh-loo-koe)
(filgrastim-ayow)
Injection
Single-Dose Prefilled Syringe

Guide to Parts

Important: The needle is covered by the gray needle cap before use.

Important

Read the Patient Information for important information you need to know about RELEUKO before using these Instructions for Use.

Before you use a RELEUKO prefilled syringe, read this important information.
Storing your prefilled syringe

- Store the prefilled syringe in the refrigerator between 36˚F to 46˚F (2˚C to 8˚C).
- Do not freeze.
- Keep the prefilled syringe in the original pack to protect from light or physical damage.
- Take the prefilled syringe out of the refrigerator 30 minutes before use and allow it to reach room temperature before preparing an injection.
- Throw away (dispose of) any prefilled syringe that has been left at room temperature for longer than 24 hours.
- After you inject your dose, throw away (dispose of) any unused RELEUKO left in the prefilled syringe. Do not save unused RELEUKO in the prefilled syringe for later use.
- Keep the RELEUKO prefilled syringe out of the reach of children.

Using your prefilled syringe

- It is important that you do not try to give the injection unless you or your caregiver has received training from your healthcare provider.
- Make sure the name RELEUKO appears on the pack and prefilled syringe label.
- Do not use a prefilled syringe after the expiration date on the label.
- Do not shake the prefilled syringe.
- Do not remove the gray needle cap from the prefilled syringe until you are ready to inject.
- Do not use the prefilled syringe if the pack is open or damaged.
- Do not use a prefilled syringe if it has been dropped on a hard surface. The prefilled syringe may be broken even if you cannot see the break. Use a new prefilled syringe.

Call your healthcare provider if you have any questions.

Step 1: Prepare

A Remove the prefilled syringe pack from the refrigerator.

Put the original pack with any unused prefilled syringes back in the refrigerator.

Remove the syringe tray from the pack. On a clean, well-lit surface, place the syringe tray at room temperature for 30 minutes before you give an injection.

- Do not use the prefilled syringe if the pack is damaged.
- Do not try to warm the prefilled syringe by using a heat source such as hot water or microwave.
- Do not leave the prefilled syringe in direct sunlight.
- Do not shake the prefilled syringe.

Open the tray by peeling away the cover. Grab the clear safety guard to remove the prefilled syringe from the tray.

For safety reasons:

- Do not grab the plunger rod.
- Do not grab the gray needle cap.

B Inspect the medicine and prefilled syringe.

Turn the prefilled syringe so you can see the medicine window and markings. Make sure the medicine in the prefilled syringe is clear and colorless.

- Do not use the prefilled syringe if:
  - The medicine is cloudy or discolored or contains flakes or particles.
  - Any part appears cracked or broken.
  - The prefilled syringe has been dropped.
  - The gray needle cap is missing or not securely attached.
  - The expiration date printed on the label has passed.
- In all cases, use a new prefilled syringe and call your healthcare provider.

C Gather all materials needed for your injection.

Wash your hands thoroughly with soap and water.

On a clean, well-lit work surface, place the:

- Prefilled syringe
- Alcohol wipe
- Cotton ball or gauze pad
- Adhesive bandage
- Sharps disposal container

Step 2: Get ready

D Prepare and clean your injection site.

You can use:

- Thigh
- Stomach area (abdomen), except for a 2-inch area right around your navel (belly button)
- Upper outer area of your buttocks (only if someone else is giving you the injection)
- Outer area of upper arm (only if someone else is giving you the injection)

Clean your injection site with an alcohol wipe.

- Let your skin dry.
- Do not touch this area again before injecting.

If you want to use the same injection site, make sure it is not the same spot on the injection site area you used for a previous injection.

- Do not inject into areas where the skin is tender, bruised, red, or hard. Avoid injecting into areas with scars or stretch marks.

E Hold the prefilled syringe by the syringe barrel. Carefully pull the gray needle cap straight off and away from your body.

- Do not remove the gray needle cap from the prefilled syringe until you are ready to inject.
- Do not twist or bend the gray needle cap.
- Do not hold the prefilled syringe by the plunger rod.
- Do not put the gray needle cap back onto the prefilled syringe.

Important: Throw the gray needle cap into the sharps disposal container.

F Check your prescription before you inject your dose.

Your healthcare provider has prescribed either a “full” syringe dose or a “partial” syringe dose of RELEUKO.

- If you are prescribed a full dose, you will inject all of the medicine from your prefilled syringe. For a full dose, go directly to Step 3: Subcutaneous (under the skin) injection.
- If you are prescribed a partial dose of RELEUKO, start with Step G below.

G Point the needle up and tap gently until the air bubbles rise to the top.

H Slowly push the plunger rod up to the line on the syringe barrel that matches your prescribed dose

As you push the plunger rod up, air and extra medicine is removed. Check to make sure the top edge of plunger stopper lines up with the syringe markings for your prescribed dose. If you remove too much medicine, get a new prefilled syringe and start again at Step 1.

- See the figure above for an example of a dose of 0.4 mL. Your dose may be different than the example shown.
- Call your healthcare provider if you have problems measuring your prescribed dose.

Step 3: Subcutaneous (under the skin) injection

I Pinch your injection site to create a firm surface.

Important: Keep skin pinched while injecting.

J Hold the pinch. Insert the needle into the skin at 45 to 90 degrees.

K Using slow and constant pressure, push the plunger rod until it reaches the bottom.

- Do not pull back the plunger rod while the needle is inserted.
- Press down slowly on the plunger as far as it will go so that the plunger head is completely between the needle guard wings.

Important: When you remove the syringe, if it looks like the medicine is still in the syringe barrel, this means you have not received a full dose. Call your healthcare provider right away.

Step 4: Finish

L Finish your injection.

- While you continue to hold the syringe, slowly let go of the plunger head.
- As you let go of the plunger head, the needle will automatically slide into the clear safety guard until the needle is completely covered.

Important: If the clear safety guard does not activate after Step L, remove the needle from the skin and throw away (discard of) the used prefilled syringe as instructed in Step M right away.

M Discard (throw away) the used prefilled syringe.

- Put the used prefilled syringe in a FDA-cleared sharps disposal container right away after use. Do not throw away (dispose of) the prefilled syringe in your household trash.
- If you do not have a FDA-cleared sharps disposal container, you may use a household container that is:
  - made of a heavy-duty plastic,
  - can be closed with a tight-fitting, puncture-resistant lid, without sharps being able to come out,
  - upright and stable during use,
  - leak-resistant, and
  - properly labeled to warn of hazardous waste inside the container.
- When your sharps disposal container is almost full, you will need to follow your community guidelines for the right way to dispose of your sharps disposal container. There may be state or local laws about how you should throw away used needles and syringes. For more information about safe sharps disposal, and for specific information about sharps disposal in the state that you live in, go to the FDA’s website at: http://www.fda.gov/safesharpsdisposal.
- Do not reuse the prefilled syringe.
- Do not recycle the prefilled syringe or sharps disposal container or throw them into household trash.

Important: Always keep the sharps disposal container out of the reach of children.

N Examine the injection site.

If there is blood, press a cotton ball or gauze pad on your injection site. Do not rub the injection site. Apply an adhesive bandage if needed.

This Instructions for Use has been approved by the U.S. Food and Drug Administration.

Manufactured by:

Kashiv BioSciences, LLC

Piscataway, NJ 08854

US License No. 2131

Distributed by:

Amneal Pharmaceuticals LLC

Bridgewater, NJ 08807

Rev. 04-2022-01

Instructions for Use (Vials)

RELEUKO® (reh-loo-koe)
(filgrastim-ayow)
Injection

Single-Dose Vial

Important

Read the Patient Information for important information you need to know about RELEUKO before using these Instructions for Use.

Before you use a RELEUKO vial, read this important information:

Storing your RELEUKO vial

- Store the vial in the refrigerator between 36˚F to 46˚F (2˚C to 8˚C).
- Do not freeze.
- Keep the vial in the original pack to protect from light or physical damage.
- Take the vial out of the refrigerator 30 minutes before use and allow it to reach room temperature before preparing an injection.
- Throw away (dispose of) any vial that has been left at room temperature for longer than 24 hours.
- After you inject your dose, throw away (dispose of) any unused RELEUKO left in the vial. Do not save unused RELEUKO in the vial for later use.
- Keep RELEUKO and all medicines out of the reach of children.

Using your vial

- It is important that you do not try to give the injection unless you or your caregiver has received training from your healthcare provider.
- Make sure the name RELEUKO appears on the pack and vial label.
- Only use the vial 1 time. Discard (throw away) the vial with any remaining RELEUKO liquid.
- Do not use a vial after the expiration date on the label.
- Do not shake the vial.
- Do not use the vial if the medicine is cloudy or discolored or contains flakes or particles.

Call your healthcare provider if you have any questions.

Step 1: Prepare

A Remove the vial from the refrigerator.

On a clean, well-lit surface, place the vial at room temperature for 30 minutes before you give an injection.

- Do not try to warm the vial by using a heat source such as hot water or microwave.
- Do not leave the vial in direct sunlight.
- Do not shake the vial.
- Use the vial only 1 time.

B Inspect the vial.

Make sure the medicine in the vial is clear and colorless.

- Do not use the vial if:
  - The medicine is cloudy or discolored or contains flakes or particles.
  - The expiration date printed on the label has passed.
- In all cases, use a new vial and call your healthcare provider.

C Gather all materials needed for your injection.

Wash your hands thoroughly with soap and water.

On a clean, well-lit work surface, place the:

- 1 Vial
- 1 Disposable syringe and needle
- 2 alcohol wipes
- 1 Cotton ball or gauze pad
- 1 Adhesive bandage
- Sharps disposal container

- Only use the disposable syringes and needles that your healthcare provider prescribes.
- Only use the syringes and needles 1 time. Discard (throw away) any used syringes and needles. See Step 5 Finish, for instructions about how to properly dispose of used syringes and needles.
- You should only use a syringe that is marked in tenths of milliliters (mL).
- Your healthcare provider will show you how to measure the correct dose of RELEUKO. This dose will be measured in milliliters (mL).

Step 2: Get Ready

D Take the cap off the vial. Clean the rubber stopper with one alcohol wipe.

E Check the carton containing the syringe. If the carton has been opened or damaged, do not use that syringe. Dispose of (throw away) that syringe in the sharps disposal container.

F Hold the syringe by the barrel with the needle cap pointing up. Carefully pull the needle cap straight off and away from your body.

Pull back on the plunger and draw air into the syringe that is the same amount (mL) as the dose of RELEUKO that your healthcare provider prescribed.

Important: Throw the needle cap into the sharps disposal container. Do not recap the needle.

G Keep the vial on the flat working surface and insert the needle straight down through the rubber stopper. Do not insert the needle through the rubber stopper more than 1 time.

H Push the plunger down and inject all the air from the syringe into the vial of RELEUKO.

I Keep the needle in the vial and turn the vial upside down. Make sure that the RELEUKO liquid is covering the tip of the needle.

J Keep the vial upside down and slowly pull back on the plunger to fill the syringe barrel with RELEUKO to the correct marking amount (mL) of medicine that matches the dose your healthcare provider prescribed.

K Keep the needle in the vial and check for air bubbles in the syringe. If there are air bubbles, gently tap the syringe barrel with your finger until the air bubbles rise to the top. Slowly push the plunger up to push the air bubbles out of the syringe.

L Keep the tip of the needle in the liquid and again pull the plunger back to the number on the syringe barrel that matches your dose. Check again for air bubbles. The air in the syringe will not hurt you, but too large an air bubble can reduce your dose of RELEUKO. If there are still air bubbles, repeat the steps above to remove them.

M Check again to make sure that you have the correct dose in the syringe. It is important that you use the exact dose prescribed by your healthcare provider. Do not remove the needle from the vial. Lay the vial down on its side with the needle still in the vial.

Step 3: Select and Prepare the Injection Site

N Prepare and clean your injection site.

You can use:

- Thigh
- Stomach area (abdomen), except for a 2-inch area right around your navel (belly button)
- Upper outer area of your buttocks (only if someone else is giving you the injection)
- Outer area of upper arm (only if someone else is giving you the injection)

Clean your injection site with a clean alcohol wipe.

- Let your skin dry.
- Do not touch this area again before injecting.
- If you want to use the same injection site, make sure it is not the same spot on the injection site area you used for a previous injection.
- Do not inject into areas where the skin is tender, bruised, red, or hard. Avoid injecting into areas with scars or stretch marks.

Step 4: Subcutaneous (under the skin) injection

O Remove the prepared syringe and needle from the vial.

P Pinch your injection site to create a firm surface.

Important: Keep skin pinched while injecting.

Q Hold the pinch. Insert the needle into the skin at a 45 to 90 degree angle.

R Using slow and constant pressure, push the plunger until it reaches the bottom.

When done, gently pull the needle out of the injection site at the same 45 to 90 degree angle used to insert it.

Step 5: Finish

S Discard (throw away) the used syringe and vial.

- Put your used syringes, needles, and vials in a FDA-cleared sharps disposal container right away after use. Do not throw away (dispose of) needles, syringes and vials in your household trash.
- If you do not have an FDA-cleared sharps disposal container, you may use a household container that:
  - is made of a heavy-duty plastic,
  - can be closed with a tight-fitting, puncture-resistant lid, without sharps being able to come out,
  - is upright and stable during use,
  - is leak-resistant, and
  - is properly labeled to warn of hazardous waste inside the container.
- When your sharps disposal container is almost full, you will need to follow your community guidelines for the right way to dispose of your sharps disposal container. There may be state or local laws about how you should throw away used syringes and needles. For more information about safe sharps disposal, and for specific information about sharps disposal in the state that you live in, go to the FDA’s website at: http://www.fda.gov/safesharpsdisposal.
- Do not reuse the syringe or vial.
- Do not recycle the syringe, vial, or sharps disposal container or throw them into household trash.

Important: Always keep the sharps disposal container out of the reach of children.

T Examine the injection site.

If there is blood, press a cotton ball or gauze pad on your injection site. Do not rub the injection site. Apply an adhesive bandage if needed.

This Instructions for Use has been approved by the U.S. Food and Drug Administration.

Manufactured by:

Kashiv BioSciences, LLC

Piscataway, NJ 08854

US License No. 2131

Distributed by:

Amneal Pharmaceuticals LLC

Bridgewater, NJ 08807

Rev. 04-2022-01